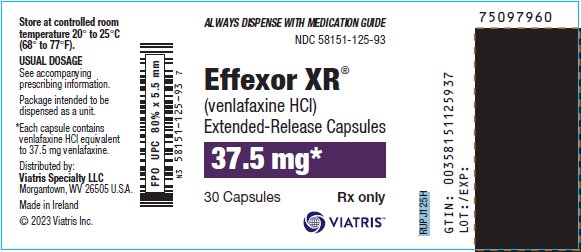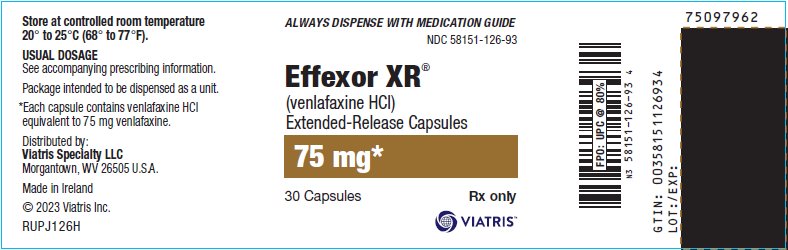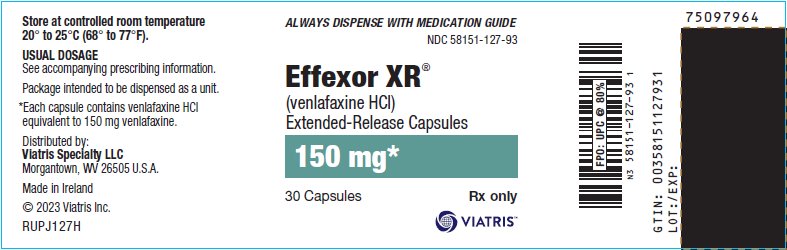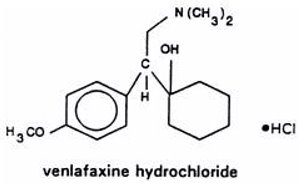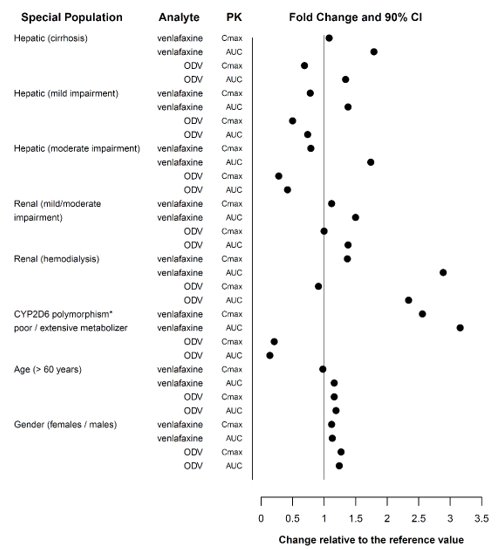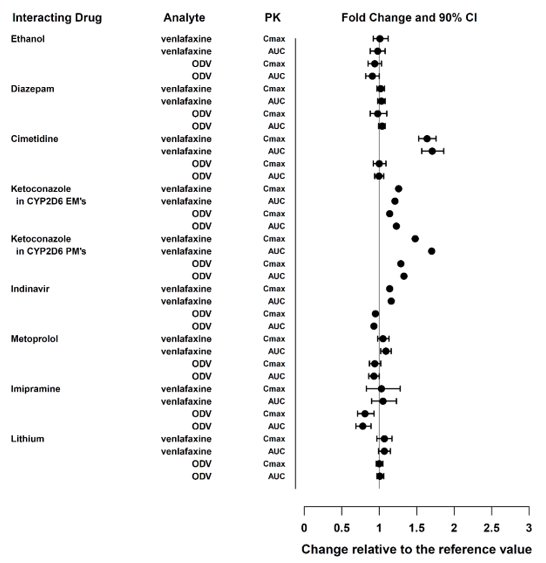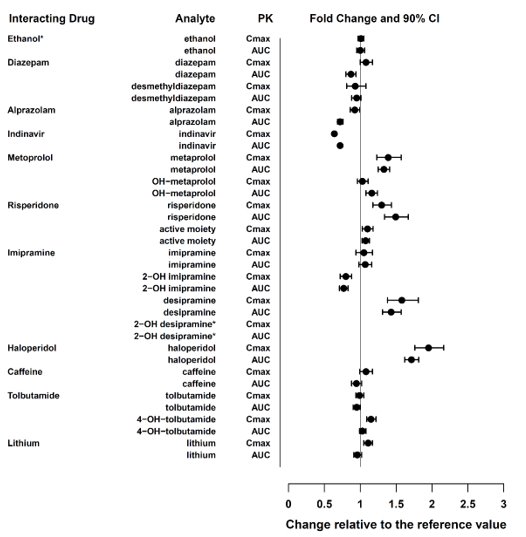 DRUG LABEL: Effexor
NDC: 58151-125 | Form: CAPSULE, EXTENDED RELEASE
Manufacturer: Viatris Specialty LLC
Category: prescription | Type: HUMAN PRESCRIPTION DRUG LABEL
Date: 20230815

ACTIVE INGREDIENTS: VENLAFAXINE HYDROCHLORIDE 37.5 mg/1 1
INACTIVE INGREDIENTS: POWDERED CELLULOSE; GELATIN, UNSPECIFIED; FERRIC OXIDE RED; TITANIUM DIOXIDE; ETHYLCELLULOSE (100 MPA.S); HYPROMELLOSE, UNSPECIFIED; HYPROMELLOSE 2910 (6 MPA.S)

HIGHLIGHTS OF PRESCRIBING INFORMATION

These highlights do not include all the information needed to use EFFEXOR XR safely and effectively. See full prescribing information for EFFEXOR XR.
EFFEXOR XR® (venlafaxine extended-release) capsules, for oral use
Initial U.S. Approval: 1997

RECENT MAJOR CHANGES

Warnings and Precautions (5.2, 5.4) 8/2023

WARNING: SUICIDAL THOUGHTS AND BEHAVIORS

See full prescribing information for complete boxed warning.

- Increased risk of suicidal thoughts and behavior in pediatric patients and young adults taking antidepressants. Closely monitor all antidepressant-treated patients for clinical worsening and emergence of suicidal thoughts and behaviors (5.1).
- Effexor XR is not approved for use in pediatric patients (8.4).

1 INDICATIONS AND USAGE

Effexor XR is a serotonin and norepinephrine reuptake inhibitor (SNRI) indicated for the treatment of adults with:

- Major Depressive Disorder (MDD) (1)
- Generalized Anxiety Disorder (GAD) (1)
- Social Anxiety Disorder (SAD) (1)
- Panic Disorder (PD) (1)

2 DOSAGE AND ADMINISTRATION

Indication | Starting Dose | Target Dose | Maximum Dose
MDD (2.2) | 37.5-75 mg/day | 75 mg/day | 225 mg/day
GAD (2.3) | 37.5-75 mg/day | 75 mg/day | 225 mg/day
SAD (2.4) | 75 mg/day | 75 mg/day | 75 mg/day
PD (2.5) | 37.5 mg/day | 75 mg/day | 225 mg/day

- Take once daily with food. Capsules should be taken whole; do not divide, crush, chew, or dissolve (2.1).
- When discontinuing treatment, reduce the dose gradually (2.10, 5.7).
- Renal impairment: reduce the total daily dose by 25% to 50% in patients with renal impairment. Reduce the total daily dose by 50% or more in patients undergoing dialysis or with severe renal impairment (2.9).
- Hepatic impairment: reduce the daily dose by 50% in patients with mild to moderate hepatic impairment. In patients with severe hepatic impairment or hepatic cirrhosis, it may be necessary to reduce the dose by more than 50% (2.8).

3 DOSAGE FORMS AND STRENGTHS

- Extended-release capsules: 37.5 mg, 75 mg, and 150 mg (3).

4 CONTRAINDICATIONS

- Hypersensitivity to venlafaxine hydrochloride, desvenlafaxine succinate, or any excipients in the Effexor XR formulation (4).
- Concomitant use of monoaminoxidase inhibitors (MAOIs) or within 14 days of discontinuing an MAOI (4, 5.2, 7.1).

5 WARNINGS AND PRECAUTIONS

- Serotonin Syndrome: Increased risk when co-administered with other serotonergic agents, but also when taken alone. If it occurs, discontinue Effexor XR and serotonergic agents and initiate supportive treatment (4, 5.2, 7.1).
- Elevated Blood Pressure: Control hypertension before initiating treatment. Monitor blood pressure regularly during treatment (5.3).
- Increased Risk of Bleeding: Concomitant use of aspirin, NSAIDs, other antiplatelet drugs, warfarin, and other anticoagulants may increase risk (5.4).
- Angle‑Closure Glaucoma: Angle-closure glaucoma has occurred in patients with untreated anatomically narrow angles, treated with antidepressants (5.5).
- Activation of Mania or Hypomania: Screen patients for bipolar disorder (5.6).
- Discontinuation Syndrome: Taper dose and monitor for discontinuation symptoms (5.7).
- Seizures: Can occur. Use cautiously in patients with seizure disorder (5.8).
- Hyponatremia: Can occur in association with SIADH (5.9).
- Interstitial Lung Disease and Eosinophilic Pneumonia: Can occur (5.12).
- Sexual Dysfunction: Effexor XR may cause symptoms of sexual dysfunction (5.13).

6 ADVERSE REACTIONS

Most common adverse reactions (incidence ≥5% and at least twice the rate of placebo): nausea, somnolence, dry mouth, sweating, abnormal ejaculation, anorexia, constipation, impotence (men), and libido decreased (6.1).

To report SUSPECTED ADVERSE REACTIONS, contact Viatris at 1-877-446-3679 (1-877-4-INFO-RX) or FDA at 1-800-FDA-1088 or www.fda.gov/medwatch.

8 USE IN SPECIFIC POPULATIONS

Pregnancy: Third trimester use may increase risk for symptoms of poor neonatal adaptation (respiratory distress, temperature instability, feeding difficulty, hypotonia, tremor, irritability) in the neonate (8.1).

FULL PRESCRIBING INFORMATION

WARNING: SUICIDAL THOUGHTS AND BEHAVIORS

Antidepressants increased the risk of suicidal thoughts and behavior in pediatric and young adult patients in short-term studies. Closely monitor all antidepressant-treated patients for clinical worsening, and emergence of suicidal thoughts and behaviors [see Warnings and Precautions (5.1)]. Effexor XR is not approved for use in pediatric patients [see Use in Specific Populations (8.4)].

1 INDICATIONS AND USAGE

Effexor XR is indicated in adults for the treatment of:

- Major Depressive Disorder (MDD) [see Clinical Studies (14.1)]
- Generalized Anxiety Disorder (GAD) [see Clinical Studies (14.2)]
- Social Anxiety Disorder (SAD) [see Clinical Studies (14.3)]
- Panic Disorder (PD) [see Clinical Studies (14.4)]

2 DOSAGE AND ADMINISTRATION

2.1 General Administration Information

Administer Effexor XR as a single dose with food, either in the morning or in the evening at approximately the same time each day [see Clinical Pharmacology (12.3)]. Swallow capsules whole with fluid. Do not divide, crush, chew, or place in water.

The capsule may also be administered by carefully opening the capsule and sprinkling the entire contents on a spoonful of applesauce. This drug/food mixture should be swallowed immediately without chewing and followed with a glass of water to ensure complete swallowing of the pellets (spheroids).

2.2 Major Depressive Disorder

For most patients, the recommended starting dose for Effexor XR is 75 mg per day, administered in a single dose. For some patients, it may be desirable to start at 37.5 mg per day for 4 to 7 days to allow new patients to adjust to the medication before increasing to 75 mg per day. Patients not responding to the initial 75 mg per day dose may benefit from dose increases to a maximum of 225 mg per day. Dose increases should be in increments of up to 75 mg per day, as needed, and should be made at intervals of not less than 4 days. In the clinical studies establishing efficacy, upward titration was permitted at intervals of 2 weeks or more.

2.3 Generalized Anxiety Disorder

For most patients, the recommended starting dose for Effexor XR is 75 mg per day, administered in a single dose. For some patients, it may be desirable to start at 37.5 mg per day for 4 to 7 days to allow new patients to adjust to the medication before increasing to 75 mg per day. Patients not responding to the initial 75 mg per day dose may benefit from dose increases to a maximum of 225 mg per day. Dose increases should be in increments of up to 75 mg per day, as needed, and should be made at intervals of not less than 4 days.

2.4 Social Anxiety Disorder (Social Phobia)

The recommended dose is 75 mg per day, administered in a single dose. There was no evidence that higher doses confer any additional benefit.

2.5 Panic Disorder

The recommended starting dose is 37.5 mg per day of Effexor XR for 7 days. Patients not responding to 75 mg per day may benefit from dose increases to a maximum of approximately 225 mg per day. Dose increases should be in increments of up to 75 mg per day, as needed, and should be made at intervals of not less than 7 days.

2.6 Screen for Bipolar Disorder Prior to Starting Effexor XR

Prior to initiating treatment with Effexor XR, screen patients for a personal or family history of bipolar disorder, mania, or hypomania [see Warnings and Precautions (5.6)].

2.7 Switching Patients from Effexor Tablets

Patients with depression who are currently being treated with Effexor may be switched to Effexor XR at the nearest equivalent dose (mg per day), e.g., 37.5 mg venlafaxine twice a day to 75 mg Effexor XR once daily. However, individual dosage adjustments may be necessary.

2.8 Dosage Recommendations for Patients with Hepatic Impairment

Reduce the Effexor XR total daily dose by 50% in patients with mild (Child-Pugh Class A) to moderate (Child-Pugh Class B) hepatic impairment. Reduce the total daily dose by 50% or more in patients with severe hepatic impairment (Child-Pugh Class C) or hepatic cirrhosis [see Use in Specific Populations (8.6)].

2.9 Dosage Recommendations for Patients with Renal Impairment

Reduce the Effexor XR total daily dose by 25% to 50% in patients with mild (CLcr 60-89 mL/min) or moderate (CLcr 30-59 mL/min) renal impairment. Reduce the total daily dose by 50% or more in patients undergoing hemodialysis or with severe renal impairment (CLcr <30 mL/min). Because there was much individual variability in clearance between patients with renal impairment, individualization of dosage is recommended in some patients [see Use in Specific Populations (8.7)].

2.10 Discontinuing Treatment with Effexor XR

A gradual reduction in the dose, rather than abrupt cessation, is recommended when discontinuing therapy with Effexor XR. In clinical studies with Effexor XR, tapering was achieved by reducing the daily dose by 75 mg at one-week intervals. Individualization of tapering may be necessary. In some patients, discontinuation may need to occur over a period of several months [see Warnings and Precautions (5.7)].

2.11 Switching Patients to or from a Monoamine Oxidase Inhibitor (MAOI) Antidepressant

At least 14 days must elapse between discontinuation of an MAOI antidepressant and initiation of Effexor XR. In addition, at least 7 days must elapse after stopping Effexor XR before starting an MAOI antidepressant [see Contraindications (4), Warnings and Precautions (5.2), and Drug Interactions (7.1)].

3 DOSAGE FORMS AND STRENGTHS

Effexor XR® is available in the following strengths:

- 37.5 mg extended-release capsule: grey cap and peach body with “W” and “Effexor XR” on the cap and “37.5” on the body
- 75 mg extended-release capsule: peach cap and body with “W” and “Effexor XR” on the cap and “75” on the body
- 150 mg extended-release capsule: dark orange cap and body with “W” and “Effexor XR” on the cap and “150” on the body

4 CONTRAINDICATIONS

Effexor XR is contraindicated in patients:

- with known hypersensitivity to venlafaxine hydrochloride, desvenlafaxine succinate or to any excipients in the formulation [see Adverse Reactions (6.2)].
- taking, or within 14 days of stopping, MAOIs (including the MAOIs linezolid and intravenous methylene blue) because of the risk of serotonin syndrome [see Dosage and Administration (2.11), Warnings and Precautions (5.2), and Drug Interactions (7.1)].

5 WARNINGS AND PRECAUTIONS

5.1 Suicidal Thoughts and Behaviors in Adolescents and Young Adults

In pooled analyses of placebo-controlled trials of antidepressant drugs (SSRIs and other antidepressant classes) that included approximately 77,000 adult patients and 4,500 pediatric patients, the incidence of suicidal thoughts and behaviors in antidepressant-treated patients age 24 years and younger was greater than in placebo-treated patients. There was considerable variation in risk of suicidal thoughts and behaviors among drugs, but there was an increased risk identified in young patients for most drugs studied. There were differences in absolute risk of suicidal thoughts and behaviors across the different indications, with the highest incidence in patients with MDD. The drug-placebo differences in the number of cases of suicidal thoughts and behaviors per 1,000 patients treated are provided in Table 1.

Table 1: Risk Differences of the Number of Patients of Suicidal Thoughts and Behaviors in the Pooled Placebo-Controlled Trials of Antidepressants in Pediatric [Effexor XR is not approved in pediatric patients.] and Adult Patients
Age Range | Drug-Placebo Difference in Number of Patients of Suicidal Thoughts and Behaviors per 1,000 Patients Treated
 | Increases Compared to Placebo
<18 years old | 14 additional patients
18-24 years old | 5 additional patients
 | Decreases Compared to Placebo
25-64 years old | 1 fewer patient
≥65 years old | 6 fewer patients

It is unknown whether the risk of suicidal thoughts and behaviors in children, adolescents, and young adults extends to longer-term use, i.e., beyond four months. However, there is substantial evidence from placebo-controlled maintenance trials in adults with MDD that antidepressants delay the recurrence of depression and that depression itself is a risk factor for suicidal thoughts and behaviors.

Monitor all antidepressant-treated patients for any indication for clinical worsening and emergence of suicidal thoughts and behaviors, especially during the initial few months of drug therapy, and at times of dosage changes. Counsel family members or caregivers of patients to monitor for changes in behavior and to alert the healthcare provider. Consider changing the therapeutic regimen, including possibly discontinuing Effexor XR, in patients whose depression is persistently worse, or who are experiencing emergent suicidal thoughts or behaviors.

5.2 Serotonin Syndrome

Serotonin-norepinephrine reuptake inhibitors (SNRIs), including Effexor XR, can precipitate serotonin syndrome, a potentially life-threatening condition. The risk is increased with concomitant use of other serotonergic drugs (including triptans, tricyclic antidepressants, fentanyl, lithium, tramadol, meperidine, methadone, tryptophan, buspirone, amphetamines, and St. John’s Wort) and with drugs that impair metabolism of serotonin, i.e., MAOIs [see Contraindications (4), Drug Interactions (7.1)]. Serotonin syndrome can also occur when these drugs are used alone.

Serotonin syndrome signs and symptoms may include mental status changes (e.g., agitation, hallucinations, delirium, coma), autonomic instability (e.g., tachycardia, labile blood pressure, dizziness, diaphoresis, flushing, hyperthermia), neuromuscular symptoms (e.g., tremor, rigidity, myoclonus, hyperreflexia, incoordination), seizures, and gastrointestinal symptoms (e.g., nausea, vomiting, diarrhea).

The concomitant use of Effexor XR with MAOIs is contraindicated. In addition, do not initiate Effexor XR in a patient being treated with MAOIs such as linezolid or intravenous methylene blue. No reports involved the administration of methylene blue by other routes (such as oral tablets or local tissue injection). If it is necessary to initiate treatment with an MAOI such as linezolid or intravenous methylene blue in a patient taking Effexor XR, discontinue Effexor XR before initiating treatment with the MAOI [see Contraindications (4), Drug Interactions (7.1)].

Monitor all patients taking Effexor XR for the emergence of serotonin syndrome. Discontinue treatment with Effexor XR and any concomitant serotonergic agents immediately if the above symptoms occur, and initiate supportive symptomatic treatment. If concomitant use of Effexor XR with other serotonergic drugs is clinically warranted, inform patients of the increased risk for serotonin syndrome and monitor for symptoms.

5.3 Elevated Blood Pressure

In controlled trials, there were dose-related increases in systolic and diastolic blood pressure, as well as cases of sustained hypertension [see Adverse Reactions (6.1)].

Monitor blood pressure before initiating treatment with Effexor XR and regularly during treatment. Control pre-existing hypertension before initiating treatment with Effexor XR. Use caution in treating patients with pre-existing hypertension or cardiovascular or cerebrovascular conditions that might be compromised by increases in blood pressure. Sustained blood pressure elevation can lead to adverse outcomes. Cases of elevated blood pressure requiring immediate treatment have been reported with Effexor XR. Consider dose reduction or discontinuation of treatment for patients who experience a sustained increase in blood pressure.

Across all clinical studies with Effexor, 1.4% of patients in the Effexor XR treated groups experienced a ≥15 mm Hg increase in supine diastolic blood pressure (SDBP) ≥105 mm Hg, compared to 0.9% of patients in the placebo groups. Similarly, 1% of patients in the Effexor XR treated groups experienced a ≥20 mm Hg increase in supine systolic blood pressure (SSBP) with blood pressure ≥180 mm Hg, compared to 0.3% of patients in the placebo groups [see Adverse Reactions (6.1)]. Treatment with Effexor XR was associated with sustained hypertension defined as SDBP ≥90 mm Hg and ≥10 mm Hg above baseline for three consecutive on-therapy visits [see Adverse Reactions (6.1)]. An insufficient number of patients received mean doses of Effexor XR over 300 mg per day in clinical studies to fully evaluate the incidence of sustained increases in blood pressure at these higher doses.

5.4 Increased Risk of Bleeding

Drugs that interfere with serotonin reuptake inhibition, including Effexor XR, may increase the risk of bleeding events, ranging from ecchymoses, hematomas, epistaxis, petechiae, and gastrointestinal hemorrhage to life-threatening hemorrhage. Concomitant use of aspirin, Nonsteroidal Anti-Inflammatory Drugs (NSAIDs), warfarin, and other anti‑coagulants or other drugs known to affect platelet function may add to this risk. Case reports and epidemiological studies (case‑control and cohort design) have demonstrated an association between use of drugs that interfere with serotonin reuptake and the occurrence of gastrointestinal bleeding. Based on data from the published observational studies, exposure to SNRIs, particularly in the month before delivery, has been associated with a less than 2-fold increase in the risk of postpartum hemorrhage [see Use in Specific Populations (8.1)].

Inform patients about the increased risk of bleeding associated with the concomitant use of Effexor XR and nonsteroidal anti-inflammatory drugs (NSAIDs), aspirin, or other drugs that affect coagulation. For patients taking warfarin, carefully monitor coagulation indices when initiating, titrating, or discontinuing Effexor XR.

5.5 Angle-Closure Glaucoma

The pupillary dilation that occurs following use of many antidepressant drugs including Effexor XR may trigger an angle closure attack in a patient with anatomically narrow angles who does not have a patent iridectomy. Avoid use of antidepressants, including Effexor XR, in patients with untreated anatomically narrow angles.

5.6 Activation of Mania or Hypomania

In patients with bipolar disorder, treating a depressive episode with Effexor XR or another antidepressant may precipitate a mixed/manic episode. Mania or hypomania was reported in Effexor XR treated patients in the premarketing studies in MDD, SAD, and PD (see Table 2). Prior to initiating treatment with Effexor XR, screen for any personal or family history of bipolar disorder, mania, or hypomania.

Table 2: Incidence (%) of Mania or Hypomania Reported in Effexor XR Treated Patients in the Premarketing Studies
Indication | Effexor XR | Placebo
MDD | 0.3 | 0.0
GAD | 0.0 | 0.2
SAD | 0.2 | 0.0
PD | 0.1 | 0.0

5.7 Discontinuation Syndrome

Discontinuation symptoms have been systematically evaluated in patients taking venlafaxine, including prospective analyses of clinical studies in GAD and retrospective surveys of studies in MDD and SAD. Abrupt discontinuation or dose reduction of venlafaxine at various doses has been found to be associated with the appearance of new symptoms, the frequency of which increased with increased dose level and with longer duration of treatment. Reported symptoms include agitation, anorexia, anxiety, confusion, impaired coordination and balance, diarrhea, dizziness, dry mouth, dysphoric mood, fasciculation, fatigue, flu-like symptoms, headaches, hypomania, insomnia, nausea, nervousness, nightmares, sensory disturbances (including shock‑like electrical sensations), somnolence, sweating, tremor, vertigo, and vomiting.

There have been postmarketing reports of serious discontinuation symptoms which can be protracted and severe. Completed suicide, suicidal thoughts, aggression and violent behavior have been observed in patients during reduction in Effexor XR dosage, including during discontinuation. Other postmarketing reports describe visual changes (such as blurred vision or trouble focusing) and increased blood pressure after stopping or reducing the dose of Effexor XR.

During marketing of Effexor XR, other SNRIs, and SSRIs, there have been reports of adverse events occurring upon discontinuation of these drugs, particularly when abrupt, including the following: irritability, lethargy, emotional lability, tinnitus, and seizures.

Patients should be monitored for these symptoms when discontinuing treatment with Effexor XR. A gradual reduction in the dose, rather than abrupt cessation, is recommended. If intolerable symptoms occur following a decrease in the dose or upon discontinuation of treatment, then resuming the previously prescribed dose may be considered. Subsequently, the healthcare provider may continue decreasing the dose, but at a more gradual rate. In some patients, discontinuation may need to occur over a period of several months [see Dosage and Administration (2.10)].

5.8 Seizures

Cases of seizure have been reported with venlafaxine therapy. Effexor XR has not been systematically evaluated in patients with seizure disorder. Effexor XR should be prescribed with caution in patients with a seizure disorder.

5.9 Hyponatremia

Hyponatremia can occur as a result of treatment with SNRIs, including Effexor XR. In many cases, the hyponatremia appears to be the result of the Syndrome of Inappropriate Antidiuretic Hormone (SIADH) secretion. Cases with serum sodium lower than 110 mmol/L have been reported. Elderly patients may be at greater risk of developing hyponatremia with SNRIs. Also, patients taking diuretics, or those who are otherwise volume-depleted, may be at greater risk [see Use in Specific Populations (8.5) and Clinical Pharmacology (12.3)]. Consider discontinuation of Effexor XR in patients with symptomatic hyponatremia, and institute appropriate medical intervention.

Signs and symptoms of hyponatremia include headache, difficulty concentrating, memory impairment, confusion, weakness, and unsteadiness, which may lead to falls. Signs and symptoms associated with more severe and/or acute cases have included hallucination, syncope, seizure, coma, respiratory arrest, and death.

5.10 Weight and Height Changes in Pediatric Patients

Weight Changes

The average change in body weight and incidence of weight loss (percentage of patients who lost 3.5% or more) in the placebo-controlled pediatric studies in MDD, GAD, and SAD are shown in Tables 3 and 4.

Table 3: Average Change in Body Weight (kg) From Beginning of Treatment in Pediatric Patients [Effexor XR is not approved for use in pediatric patients.] in Double-blind, Placebo-controlled Studies of Effexor XR
Indication (Duration) | Effexor XR | Placebo
MDD and GAD (4 pooled studies, 8 weeks) | -0.45 (n = 333) | +0.77 (n = 333)
SAD (16 weeks) | -0.75 (n = 137) | +0.76 (n = 148)

Table 4: Incidence (%) of Pediatric Patients [Effexor XR is not approved for use in pediatric patients.] Experiencing Weight Loss (3.5% or more) in Double-blind, Placebo-controlled Studies of Effexor XR
Indication (Duration) | Effexor XR | Placebo
MDD and GAD (4 pooled studies, 8 weeks) | 18 [p <0.001 versus placebo] (n = 333) | 3.6 (n = 333)
SAD (16 weeks) | 47 (n = 137) | 14 (n = 148)

Weight loss was not limited to patients with anorexia [see Warnings and Precautions (5.11)].

The risks associated with longer term Effexor XR use were assessed in an open-label MDD study of children and adolescents who received Effexor XR for up to six months. The children and adolescents in the study had increases in weight that were less than expected, based on data from age- and sex-matched peers. The difference between observed weight gain and expected weight gain was larger for children (<12 years old) than for adolescents (≥12 years old).

Effexor XR is not approved for use in pediatric patients [Use in Specific Populations (8.4)].

Height Changes

Table 5 shows the average height increase in pediatric patients in the short‑term, placebo-controlled MDD, GAD, and SAD studies. The differences in height increases in GAD and MDD studies were most notable in patients younger than 12 years old.

Table 5: Average Height Increases (cm) in Pediatric Patients [Effexor XR is not approved for use in pediatric patients.] in Placebo-controlled Studies of Effexor XR
Indication (Duration) | Effexor XR | Placebo
MDD (8 weeks) | 0.8 (n = 146) | 0.7 (n = 147)
GAD (8 weeks) | 0.3 [p = 0.041] (n = 122) | 1.0 (n = 132)
SAD (16 weeks) | 1.0 (n = 109) | 1.0 (n = 112)

In the six-month, open-label MDD study, children and adolescents had height increases that were less than expected, based on data from age- and sex-matched peers. The difference between observed and expected growth rates was larger for children (<12 years old) than for adolescents (≥12 years old) [see Use in Specific Populations (8.4)].

5.11 Appetite Changes in Pediatric Patients

Decreased appetite (reported as anorexia) was more commonly observed in Effexor XR treated patients versus placebo-treated patients in the premarketing evaluation of Effexor XR for MDD, GAD, and SAD (see Table 6).

Effexor XR is not approved for use in pediatric patients [see Use in Specific Populations (8.4)].

Table 6: Incidence (%) of Decreased Appetite and Associated Discontinuation Rates [The discontinuation rates for weight loss were 0.7% for patients receiving either Effexor XR or placebo.] (%) in Pediatric Patients [Effexor XR is not approved for use in pediatric patients.] in Placebo-controlled Studies of Effexor XR
Indication | Effexor XR |  | Placebo
(Duration) | Incidence | Discontinuation | Incidence | Discontinuation
MDD and GAD (pooled, 8 weeks) | 10 | 0.0 | 3 | –
SAD (16 weeks) | 22 | 0.7 | 3 | 0.0

5.12 Interstitial Lung Disease and Eosinophilic Pneumonia

Interstitial lung disease and eosinophilic pneumonia associated with venlafaxine therapy have been rarely reported. The possibility of these events should be considered in Effexor XR‑treated patients who present with progressive dyspnea, cough or chest discomfort. Such patients should undergo a prompt medical evaluation, and discontinuation of Effexor XR should be considered.

5.13 Sexual Dysfunction

Use of SNRIs, including Effexor XR, may cause symptoms of sexual dysfunction [see Adverse Reactions (6.1)]. In male patients, SNRI use may result in ejaculatory delay or failure, decreased libido, and erectile dysfunction. In female patients, SNRI use may result in decreased libido and delayed or absent orgasm. It is important for prescribers to inquire about sexual function prior to initiation of Effexor XR and to inquire specifically about changes in sexual function during treatment, because sexual function may not be spontaneously reported. When evaluating changes in sexual function, obtaining a detailed history (including timing of symptom onset) is important because sexual symptoms may have other causes, including the underlying psychiatric disorder. Discuss potential management strategies to support patients in making informed decisions about treatment.

6 ADVERSE REACTIONS

The following adverse reactions are discussed in more detail in other sections of the labeling:

- Hypersensitivity [see Contraindications (4)]
- Suicidal Thoughts and Behaviors in Adolescents and Young Adults [see Warnings and Precautions (5.1)]
- Serotonin Syndrome [see Warnings and Precautions (5.2)]
- Elevated Blood Pressure [see Warnings and Precautions (5.3)]
- Increased Risk of Bleeding [see Warnings and Precautions (5.4)]
- Angle-Closure Glaucoma [see Warnings and Precautions (5.5)]
- Activation of Mania/Hypomania [see Warnings and Precautions (5.6)]
- Discontinuation Syndrome [see Warnings and Precautions (5.7)]
- Seizure [see Warnings and Precautions (5.8)]
- Hyponatremia [see Warnings and Precautions (5.9)]
- Weight and Height Changes in Pediatric Patients [see Warnings and Precautions (5.10)]
- Appetite Changes in Pediatric Patients [see Warnings and Precautions (5.11)]
- Interstitial Lung Disease and Eosinophilic Pneumonia [see Warnings and Precautions (5.12)]
- Sexual Dysfunction [see Warnings and Precautions (5.13)]

6.1 Clinical Studies Experience

Because clinical trials are conducted under widely varying conditions, adverse reaction rates observed in the clinical trials of a drug cannot be directly compared to rates in the clinical studies of another drug and may not reflect the rates observed in clinical practice.

Most Common Adverse Reactions

The most commonly observed adverse reactions in the clinical study database in Effexor XR treated patients in MDD, GAD, SAD, and PD (incidence ≥5% and at least twice the rate of placebo) were: nausea (30.0%), somnolence (15.3%), dry mouth (14.8%), sweating (11.4%), abnormal ejaculation (9.9%), anorexia (9.8%), constipation (9.3%), impotence (5.3%), and decreased libido (5.1%).

Adverse Reactions Reported as Reasons for Discontinuation of Treatment

Combined across short-term, placebo-controlled premarketing studies for all indications, 12% of the 3,558 patients who received Effexor XR (37.5-225 mg) discontinued treatment due to an adverse experience, compared with 4% of the 2,197 placebo-treated patients in those studies.

The most common adverse reactions leading to discontinuation in ≥1% of the Effexor XR treated patients in the short-term studies (up to 12 weeks) across indications are shown in Table 7.

Table 7: Incidence (%) of Patients Reporting Adverse Reactions Leading to Discontinuation in Placebo-controlled Clinical Studies (up to 12 Weeks Duration)
Body System Adverse Reaction | Effexor XR n = 3,558 | Placebo n = 2,197
Body as a whole
Asthenia | 1.7 | 0.5
Headache | 1.5 | 0.8
Digestive system
Nausea | 4.3 | 0.4
Nervous system
Dizziness | 2.2 | 0.8
Insomnia | 2.1 | 0.6
Somnolence | 1.7 | 0.3
Skin and appendages | 1.5 | 0.6
Sweating | 1.0 | 0.2

Common Adverse Reactions in Placebo-controlled Studies

The number of patients receiving multiple doses of Effexor XR during the premarketing assessment for each approved indication is shown in Table 8. The conditions and duration of exposure to venlafaxine in all development programs varied greatly, and included (in overlapping categories) open and double-blind studies, uncontrolled and controlled studies, inpatient (Effexor only) and outpatient studies, fixed-dose, and titration studies.

Table 8: Patients Receiving Effexor XR in Premarketing Clinical Studies
Indication | Effexor XR
MDD | 705 [In addition, in the premarketing assessment of Effexor, multiple doses were administered to 2,897 patients in studies for MDD.]
GAD | 1,381
SAD | 819
PD | 1,314

The incidences of common adverse reactions (those that occurred in ≥2% of Effexor XR treated patients [357 MDD patients, 1,381 GAD patients, 819 SAD patients, and 1,001 PD patients] and more frequently than placebo) in Effexor XR treated patients in short-term, placebo-controlled, fixed- and flexible-dose clinical studies (doses 37.5 to 225 mg per day) are shown in Table 9.

The adverse reaction profile did not differ substantially between the different patient populations.

Table 9: Common Adverse Reactions: Percentage of Patients Reporting Adverse Reactions (≥2% and > placebo) in Placebo-controlled Studies (up to 12 Weeks Duration) across All Indications
Body System Adverse Reaction | Effexor XR n = 3,558 | Placebo n = 2,197
Body as a whole
Asthenia | 12.6 | 7.8
Cardiovascular system
Hypertension | 3.4 | 2.6
Palpitation | 2.2 | 2.0
Vasodilatation | 3.7 | 1.9
Digestive system
Anorexia | 9.8 | 2.6
Constipation | 9.3 | 3.4
Diarrhea | 7.7 | 7.2
Dry mouth | 14.8 | 5.3
Nausea | 30.0 | 11.8
Vomiting | 4.3 | 2.7
Nervous system
Abnormal dreams | 2.9 | 1.4
Dizziness | 15.8 | 9.5
Insomnia | 17.8 | 9.5
Libido decreased | 5.1 | 1.6
Nervousness | 7.1 | 5.0
Paresthesia | 2.4 | 1.4
Somnolence | 15.3 | 7.5
Tremor | 4.7 | 1.6
Respiratory system
Yawn | 3.7 | 0.2
Skin and appendages
Sweating (including night sweats) | 11.4 | 2.9
Special senses
Abnormal vision | 4.2 | 1.6
Urogenital system
Abnormal ejaculation/orgasm (men) [Percentages based on the number of men (Effexor XR, n = 1,440; placebo, n = 923)] | 9.9 | 0.5
Anorgasmia (men) | 3.6 | 0.1
Anorgasmia (women) [Percentages based on the number of women (Effexor XR, n = 2,118; placebo, n = 1,274)] | 2.0 | 0.2
Impotence (men) | 5.3 | 1.0

Other Adverse Reactions Observed in Clinical Studies

Body as a Whole – Photosensitivity reaction, chills

Cardiovascular System – Postural hypotension, syncope, hypotension, tachycardia

Digestive System – Gastrointestinal hemorrhage [see Warnings and Precautions (5.4)], bruxism

Hemic/Lymphatic System – Ecchymosis [see Warnings and Precautions (5.4)]

Metabolic/Nutritional – Hypercholesterolemia, weight gain [see Warnings and Precautions (5.10)], weight loss [see Warnings and Precautions (5.10)]

Nervous System – Seizures [see Warnings and Precautions (5.8)], manic reaction [see Warnings and Precautions (5.6)], agitation, confusion, akathisia, hallucinations, hypertonia, myoclonus, depersonalization, apathy

Skin and Appendages – Urticaria, pruritus, rash, alopecia

Special Senses – Mydriasis, abnormality of accommodation, tinnitus, taste perversion

Urogenital System – Urinary retention, urination impaired, urinary incontinence, urinary frequency increased, menstrual disorders associated with increased bleeding or increased irregular bleeding (e.g., menorrhagia, metrorrhagia)

Vital Sign Changes

In placebo-controlled premarketing studies, there were increases in mean blood pressure (see Table 10). Across most indications, a dose-related increase in mean supine systolic and diastolic blood pressure was evident in patients treated with Effexor XR. Across all clinical studies in MDD, GAD, SAD and PD, 1.4% of patients in the Effexor XR groups experienced an increase in SDBP of ≥15 mm Hg along with a blood pressure ≥105 mm Hg, compared to 0.9% of patients in the placebo groups. Similarly, 1% of patients in the Effexor XR groups experienced an increase in SSBP of ≥20 mm Hg with a blood pressure ≥180 mm Hg, compared to 0.3% of patients in the placebo groups.

Table 10: Final On-therapy Mean Changes from Baseline in Supine Systolic (SSBP) and Diastolic (SDBP) Blood Pressure (mm Hg) in Placebo-controlled Studies
 | Effexor XR |  |  |  | Placebo
Indication | ≤75 mg per day |  | >75 mg per day
(Duration) | SSBP | SDBP | SSBP | SDBP | SSBP | SDBP
MDD
(8-12 weeks) | -0.28 | 0.37 | 2.93 | 3.56 | -1.08 | -0.10
GAD
(8 weeks) | -0.28 | 0.02 | 2.40 | 1.68 | -1.26 | -0.92
(6 months) | 1.27 | -0.69 | 2.06 | 1.28 | -1.29 | -0.74
SAD
(12 weeks) | -0.29 | -1.26 | 1.18 | 1.34 | -1.96 | -1.22
(6 months) | -0.98 | -0.49 | 2.51 | 1.96 | -1.84 | -0.65
PD
(10-12 weeks) | -1.15 | 0.97 | -0.36 | 0.16 | -1.29 | -0.99

Effexor XR treatment was associated with sustained hypertension (defined as Supine Diastolic Blood Pressure [SDBP] ≥90 mm Hg and ≥10 mm Hg above baseline for three consecutive on-therapy visits (see Table 11). An insufficient number of patients received mean doses of Effexor XR over 300 mg per day in clinical studies to fully evaluate the incidence of sustained increases in blood pressure at these higher doses.

Table 11: Sustained Elevations in SDBP in Effexor XR Premarketing Studies
Indication | Dose Range (mg per day) | Incidence (%)
MDD | 75-375 [Maximum recommended dosage for Effexor XR is 225 mg once daily.] | 19/705 (3)
GAD | 37.5-225 | 5/1011 (0.5)
SAD | 75-225 | 5/771 (0.6)
PD | 75-225 | 9/973 (0.9)

Effexor XR was associated with mean increases in pulse rate compared with placebo in premarketing placebo-controlled studies (see Table 12) [see Warnings and Precautions (5.3, 5.4)].

Table 12: Approximate Mean Final On-therapy Increase in Pulse Rate (beats/min) in Effexor XR Premarketing Placebo-controlled Studies (up to 12 Weeks Duration)
Indication (Duration) | Effexor XR | Placebo
MDD (12 weeks) | 2 | 1
GAD (8 weeks) | 2 | <1
SAD (12 weeks) | 3 | 1
PD (12 weeks) | 1 | <1

Laboratory Changes

Serum Cholesterol

Effexor XR was associated with mean final increases in serum cholesterol concentrations compared with mean final decreases for placebo in premarketing MDD, GAD, SAD and PD clinical studies (Table 13).

Table 13: Mean Final On-therapy Changes in Cholesterol Concentrations (mg/dL) in Effexor XR Premarketing Studies
Indication (Duration) | Effexor XR | Placebo
MDD
(12 weeks) | +1.5 | -7.4
GAD
(8 weeks) | +1.0 | -4.9
(6 months) | +2.3 | -7.7
SAD
(12 weeks) | +7.9 | -2.9
(6 months) | +5.6 | -4.2
PD
(12 weeks) | +5.8 | -3.7

Effexor XR (venlafaxine hydrochloride) extended-release capsules treatment for up to 12 weeks in premarketing placebo-controlled trials for major depressive disorder was associated with a mean final on-therapy increase in serum cholesterol concentration of approximately 1.5 mg/dL compared with a mean final decrease of 7.4 mg/dL for placebo. Effexor XR treatment for up to 8 weeks and up to 6 months in premarketing placebo-controlled GAD trials was associated with mean final on-therapy increases in serum cholesterol concentration of approximately 1.0 mg/dL and 2.3 mg/dL, respectively while placebo subjects experienced mean final decreases of 4.9 mg/dL and 7.7 mg/dL, respectively. Effexor XR treatment for up to 12 weeks and up to 6 months in premarketing placebo-controlled Social Anxiety Disorder trials was associated with mean final on-therapy increases in serum cholesterol concentration of approximately 7.9 mg/dL and 5.6 mg/dL, respectively, compared with mean final decreases of 2.9 and 4.2 mg/dL, respectively, for placebo. Effexor XR treatment for up to 12 weeks in premarketing placebo-controlled panic disorder trials was associated with mean final on-therapy increases in serum cholesterol concentration of approximately 5.8 mg/dL compared with a mean final decrease of 3.7 mg/dL for placebo.

Patients treated with Effexor (immediate-release) for at least 3 months in placebo-controlled 12-month extension trials had a mean final on-therapy increase in total cholesterol of 9.1 mg/dL compared with a decrease of 7.1 mg/dL among placebo-treated patients. This increase was duration dependent over the study period and tended to be greater with higher doses. Clinically relevant increases in serum cholesterol, defined as 1) a final on-therapy increase in serum cholesterol ≥50 mg/dL from baseline and to a value ≥261 mg/dL, or 2) an average on-therapy increase in serum cholesterol ≥50 mg/dL from baseline and to a value ≥261 mg/dL, were recorded in 5.3% of venlafaxine-treated patients and 0.0% of placebo-treated patients.

Serum Triglycerides

Effexor XR was associated with mean final on-therapy increases in fasting serum triglycerides compared with placebo in premarketing clinical studies of SAD and PD up to 12 weeks (pooled data) and 6 months duration (Table 14).

Table 14: Mean Final On-therapy Increases in Triglyceride Concentrations (mg/dL) in Effexor XR Premarketing Studies
Indication (Duration) | Effexor XR | Placebo
SAD (12 weeks) | 8.2 | 0.4
SAD (6 months) | 11.8 | 1.8
PD (12 weeks) | 5.9 | 0.9
PD (6 months) | 9.3 | 0.3

6.2 Postmarketing Experience

The following adverse reactions have been identified during post-approval use of Effexor XR. Because these reactions are reported voluntarily from a population of uncertain size, it is not always possible to reliably estimate their frequency or establish a causal relationship to drug exposure.

Body as a Whole – Anaphylaxis, angioedema

Cardiovascular System – QT prolongation, ventricular fibrillation, ventricular tachycardia (including torsade de pointes), takotsubo cardiomyopathy

Digestive System – Pancreatitis

Hemic/Lymphatic System – Mucous membrane bleeding [see Warnings and Precautions (5.4)], blood dyscrasias (including agranulocytosis, aplastic anemia, neutropenia and pancytopenia), prolonged bleeding time, thrombocytopenia

Metabolic/Nutritional – Hyponatremia [see Warnings and Precautions (5.9)], Syndrome of Inappropriate Antidiuretic Hormone (SIADH) secretion [see Warnings and Precautions (5.9)], abnormal liver function tests, hepatitis, prolactin increased

Musculoskeletal – Rhabdomyolysis

Nervous System – Neuroleptic Malignant Syndrome (NMS) [see Warnings and Precautions (5.2)], serotonergic syndrome [see Warnings and Precautions (5.2)], delirium, extrapyramidal reactions (including dystonia and dyskinesia), impaired coordination and balance, tardive dyskinesia

Respiratory, Thoracic and Mediastinal Disorders – Anosmia, dyspnea, hyposmia, interstitial lung disease, pulmonary eosinophilia [see Warnings and Precautions (5.12)]

Skin and Appendages – Stevens-Johnson syndrome, toxic epidermal necrolysis, erythema multiforme

Special Senses – Angle-closure glaucoma [see Warnings and Precautions (5.5)]

7 DRUG INTERACTIONS

7.1 Drugs Having Clinically Important Interactions with Effexor XR

Table 15: Clinically Important Drug Interactions with Effexor XR
Monoamine Oxidase Inhibitors (MAOI)
Clinical Impact | The concomitant use of SNRIs, including Effexor XR, with MAOIs increases the risk of serotonin syndrome.
Intervention | Concomitant use of Effexor XR is contraindicated in patients taking MAOIs, including MAOIs such as linezolid or intravenous methylene blue [see Dosage and Administration (2.11), Contraindications (4) and Warnings and Precautions (5.2)].
Other Serotonergic Drugs
Clinical Impact | Concomitant use of Effexor XR with other serotonergic drugs (including other SNRIs, SSRIs, triptans, tricyclic antidepressants, opioids, lithium, buspirone, amphetamines, tryptophan, and St. John's Wort) increases the risk of serotonin syndrome.
Intervention | Monitor for symptoms of serotonin syndrome when Effexor XR is used concomitantly with other drugs that may affect the serotonergic neurotransmitter systems. If serotonin syndrome occurs, consider discontinuation of Effexor XR and/or concomitant serotonergic drugs [see Dosage and Administration (2.11) and Warnings and Precautions (5.2)].
Drugs that Interfere with Hemostasis
Clinical Impact | Concomitant use of Effexor XR with an antiplatelet or anticoagulant drug may potentiate the risk of bleeding. This may be due to the effect of Effexor XR on the release of serotonin by platelets.
Intervention | Closely monitor for bleeding for patients receiving an antiplatelet or anticoagulant drug when Effexor XR is initiated or discontinued [see Warnings and Precautions (5.4)].
Effect of CYP3A Inhibitors
Clinical Impact | Concomitant use of a CYP3A inhibitor increases the Cmax and AUC of venlafaxine and O-desmethylvenlafaxine (ODV) [see Clinical Pharmacology (12.3)], which may increase the risk of toxicity of Effexor XR.
Intervention | Consider reducing the dose of Effexor XR.
CYP2D6 Substrates
Clinical Impact | Concomitant use of Effexor XR increases Cmax and AUC of a CYP2D6 substrate, which may increase the risk of toxicity of the CYP2D6 substrate [see Clinical Pharmacology (12.3)].
Intervention | Consider reduction in dose of concomitant CYP2D6 substrates.

7.2 Other Drug Interactions with Effexor XR

Central Nervous System (CNS)-Active Drugs

The risk of using venlafaxine concomitantly with other CNS-active drugs (including alcohol) has not been systematically evaluated. Consequently, caution is advised when Effexor XR is taken concomitantly in combination with other CNS-active drugs.

Weight Loss Agents

Concomitant use of Effexor XR and weight loss agents is not recommended. The safety and efficacy of venlafaxine therapy in combination with weight loss agents, including phentermine, have not been established. Effexor XR is not indicated for weight loss alone or in combination with other products.

Laboratory Test Interference

False-positive urine immunoassay screening tests for phencyclidine (PCP) and amphetamine have been reported in patients taking venlafaxine due to lack of specificity of the screening tests. False-positive test results may be expected for several days following discontinuation of venlafaxine therapy. Confirmatory tests, such as gas chromatography/mass spectrometry, will distinguish venlafaxine from PCP and amphetamine.

8 USE IN SPECIFIC POPULATIONS

8.1 Pregnancy

Pregnancy Exposure Registry

There is a pregnancy exposure registry that monitors pregnancy outcomes in women exposed to antidepressants, including Effexor XR, during pregnancy. Healthcare providers are encouraged to register patients by calling the National Pregnancy Registry for Antidepressants at 1-844-405-6185 or visiting online at https://womensmentalhealth.org/clinical-and-research-programs/pregnancyregistry/antidepressants/.

Risk Summary

Based on data from published observational studies, exposure to SNRIs, particularly in the month before delivery, has been associated with a less than 2-fold increase in the risk of postpartum hemorrhage [see Warnings and Precautions (5.4) and Clinical Considerations].

Available data from published epidemiologic studies on venlafaxine use in pregnant women have not identified a drug-associated risk of major birth defects, miscarriage or adverse fetal outcomes (see Data). Available data from observational studies with venlafaxine have identified a potential increased risk for preeclampsia when used during mid to late pregnancy; exposure to SNRIs near delivery may increase the risk for postpartum hemorrhage (see Clinical Considerations). There are risks associated with untreated depression in pregnancy and poor neonatal adaptation in newborns with exposure to SNRIs, including Effexor XR, during pregnancy (see Clinical Considerations).

In animal studies, there was no evidence of malformations or fetotoxicity following administration of venlafaxine during organogenesis at doses up to 2.5 times (rat) or 4 times (rabbit) the maximum recommended human daily dose on a mg/m^2 basis. Postnatal mortality and decreased pup weights were observed following venlafaxine administration to pregnant rats during gestation and lactation at 2.5 times (mg/m^2) the maximum human daily dose.

The estimated background risk of major birth defects and miscarriage for the indicated populations is unknown. All pregnancies have a background risk of birth defect, loss, or other adverse outcomes. In the U.S. general population, the estimated background risk of major birth defects and miscarriage in clinically recognized pregnancies is 2 to 4% and 15 to 20%, respectively.

Clinical Considerations

Disease-Associated Maternal and/or Embryo/Fetal Risk

Women who discontinue antidepressants during pregnancy are more likely to experience a relapse of major depression than women who continue antidepressants. This finding is from a prospective, longitudinal study that followed 201 pregnant women with a history of major depression who were euthymic and taking antidepressants at the beginning of pregnancy. Consider the risk of untreated depression when discontinuing or changing treatment with antidepressant medication during pregnancy and postpartum.

Maternal Adverse Reactions

Exposure to Effexor XR in mid to late pregnancy may increase the risk for preeclampsia, and exposure to Effexor XR in the month before delivery may be associated with an increased risk of postpartum hemorrhage [see Warnings and Precautions (5.4)].

Fetal/Neonatal Adverse Reactions

Neonates exposed to SNRIs late in the third trimester have developed complications requiring prolonged hospitalization, respiratory support, and tube feeding. Such complications can arise immediately upon delivery. Reported clinical findings have included respiratory distress, cyanosis, apnea, seizures, temperature instability, feeding difficulty, vomiting, hypoglycemia, hypotonia, hypertonia, hyperreflexia, tremors, jitteriness, irritability, and constant crying. These findings are consistent with either a direct toxic effect of SNRIs or possibly a drug discontinuation syndrome. It should be noted that, in some cases, the clinical picture is consistent with serotonin syndrome [see Warnings and Precautions (5.2)]. Monitor neonates who were exposed to Effexor XR in the third trimester of pregnancy for drug discontinuation syndrome (see Data).

Data

Human Data

Published epidemiological studies of pregnant women exposed to venlafaxine have not established an increased risk of major birth defects, miscarriage or other adverse developmental outcomes. Methodological limitations may both fail to identify true findings and also identify findings that are not true.

Retrospective cohort studies based on claims data have shown an association between venlafaxine use and preeclampsia, compared to depressed women who did not take an antidepressant during pregnancy. One study that assessed venlafaxine exposure in the second trimester or first half of the third trimester and preeclampsia showed an increased risk compared to unexposed depressed women (adjusted [adj] RR 1.57, 95% confidence interval [CI] 1.29-1.91). Preeclampsia was observed at venlafaxine doses equal to or greater than 75 mg per day and a duration of treatment >30 days. Another study that assessed venlafaxine exposure in gestational weeks 10-20 and preeclampsia showed an increased risk at doses equal to or greater than 150 mg per day. Available data are limited by possible outcome misclassification and possible confounding due to depression severity and other confounders.

Retrospective cohort studies based on claims data have suggested an association between venlafaxine use near the time of delivery or through delivery and postpartum hemorrhage. One study showed an increased risk for postpartum hemorrhage when venlafaxine exposure occurred through delivery, compared to unexposed depressed women (adj RR 2.24 [95% CI 1.69-2.97]). There was no increased risk in women who were exposed to venlafaxine earlier in pregnancy. Limitations of this study include possible confounding due to depression severity and other confounders. Another study showed an increased risk for postpartum hemorrhage when SNRI exposure occurred for at least 15 days in the last month of pregnancy or through delivery, compared to unexposed women (adj RR 1.64-1.76). The results of this study may be confounded by the effects of depression.

Animal Data

Venlafaxine did not cause malformations in offspring of rats or rabbits given doses up to 2.5 times (rat) or 4 times (rabbit) the maximum recommended human daily dose on a mg/m^2 basis. However, in rats, there was a decrease in pup weight, an increase in stillborn pups, and an increase in pup deaths during the first 5 days of lactation, when dosing began during pregnancy and continued until weaning. The cause of these deaths is not known. These effects occurred at 2.5 times (mg/m^2) the maximum human daily dose. The no effect dose for rat pup mortality was 0.25 times the human dose on a mg/m^2 basis.

When desvenlafaxine succinate, the major metabolite of venlafaxine, was administered orally to pregnant rats and rabbits during the period of organogenesis at doses up to 300 mg/kg/day and 75 mg/kg/day, respectively, no fetal malformations were observed. These doses were associated with a plasma exposure (AUC) 19 times (rats) and 0.5 times (rabbits) the AUC exposure at an adult human dose of 100 mg per day. However, fetal weights were decreased and skeletal ossification was delayed in rats in association with maternal toxicity at the highest dose, with an AUC exposure at the no-effect dose that is 4.5-times the AUC exposure at an adult human dose of 100 mg per day.

8.2 Lactation

Risk Summary

Data from published literature report the presence of venlafaxine and its active metabolite in human milk and have not shown adverse reactions in breastfed infants (see Data). There are no data on the effects of venlafaxine on milk production.

The developmental and health benefits of breastfeeding should be considered along with the mother’s clinical need for Effexor XR and any potential adverse effects on the breastfed child from Effexor XR or from the underlying maternal condition.

Data

In a lactation study conducted in 11 breastfeeding women (at a mean of 20.1 months post-partum) who were taking a mean daily dose of 194.3 mg of venlafaxine and in a lactation study conducted in 6 breastfeeding women who were taking a daily dose of 225 mg to 300 mg of venlafaxine (at a mean of 7 months post-partum), the estimated mean relative infant dose was 8.1% and 6.4% based on the sum of venlafaxine and its major metabolite, desvenlafaxine. No adverse reactions were seen in the infants.

8.4 Pediatric Use

Safety and effectiveness of Effexor XR in pediatric patients have not been established.

Two placebo-controlled trials in 766 pediatric patients with MDD and two placebo-controlled trials in 793 pediatric patients with GAD have been conducted with Effexor XR, and the data were not sufficient to support use in pediatric patients.

In the studies conducted in pediatric patients ages 6 to 17 years, the occurrence of blood pressure and cholesterol increases was considered to be clinically relevant in pediatric patients and was similar to that observed in adult patients [see Warnings and Precautions (5.3), Adverse Reactions (6.1)]. The following adverse reactions were also observed in pediatric patients: abdominal pain, agitation, dyspepsia, ecchymosis, epistaxis, and myalgia.

Although no studies have been designed to primarily assess Effexor XR’s impact on the growth, development, and maturation of children and adolescents, the studies that have been done suggest that Effexor XR may adversely affect weight and height [see Warnings and Precautions (5.10, 5.11)]. Decreased appetite and weight loss were observed in placebo-controlled studies of pediatric patients 6 to 17 years.

In pediatric clinical studies, the adverse reaction, suicidal ideation, was observed. Antidepressants increased the risk of suicidal thoughts and behaviors in pediatric patients [see Boxed Warning, Warnings and Precautions (5.1)].

8.5 Geriatric Use

The percentage of patients in clinical studies for Effexor XR for MDD, GAD, SAD, and PD who were 65 years of age or older are shown in Table 16.

Table 16: Percentage (and Number of Patients Studied) of Patients 65 Years of Age and Older by Indication [In addition, in the premarketing assessment of Effexor (immediate-release), 12% (357/2,897) of patients were ≥ 65 years of age.]
Indication | Effexor XR
MDD | 4 (14/357)
GAD | 6 (77/1,381)
SAD | 1 (10/819)
PD | 2 (16/1,001)

No overall differences in effectiveness or safety were observed between geriatric patients and younger patients, and other reported clinical experience generally has not identified differences in response between the elderly and younger patients. However, greater sensitivity of some older individuals cannot be ruled out. SSRIs and SNRIs, including Effexor XR, have been associated with cases of clinically significant hyponatremia in elderly patients, who may be at greater risk for this adverse event [see Warnings and Precautions (5.9)].

The pharmacokinetics of venlafaxine and ODV are not substantially altered in the elderly [see Clinical Pharmacology (12.3)] (see Figure 1). No dose adjustment is recommended for the elderly on the basis of age alone, although other clinical circumstances, some of which may be more common in the elderly, such as renal or hepatic impairment, may warrant a dose reduction [see Dosage and Administration (2.8, 2.9)].

8.6 Hepatic Impairment

Dosage adjustment is recommended in patients with mild (Child-Pugh Class A), moderate (Child-Pugh Class B), or severe (Child-Pugh Class C) hepatic impairment or hepatic cirrhosis [see Dosage and Administration (2.8) and Clinical Pharmacology (12.3)].

8.7 Renal Impairment

Dosage adjustment is recommended in patients with mild (CLcr = 60-89 mL/min), moderate (CLcr = 30-59 mL/min), or severe (CLcr <30 mL/min) renal impairment, and in patients undergoing hemodialysis [see Dosage and Administration (2.9) and Clinical Pharmacology (12.3)].

9 DRUG ABUSE AND DEPENDENCE

9.1 Controlled Substance

Effexor XR contains venlafaxine which is not a controlled substance.

9.2 Abuse

Abuse is the intentional, non-therapeutic use of a drug, even once, for its desirable psychological or physiological effects.

While venlafaxine has not been systematically studied in clinical studies for its potential for abuse, there was no indication of drug-seeking behavior in the clinical studies. However, it is not possible to predict on the basis of premarketing experience the extent to which a CNS-active drug will be misused, diverted, and/or abused once marketed. Consequently, providers should carefully evaluate patients for history of drug abuse and follow such patients closely, observing them for signs of misuse or abuse of venlafaxine (e.g., development of tolerance, incrementation of dose, drug-seeking behavior).

9.3 Dependence

Physical dependence is a state that develops as a result of physiological adaptation in response to repeated drug use, manifested by withdrawal signs and symptoms after abrupt discontinuation or a significant dose reduction of a drug.

In vitro studies revealed that venlafaxine has virtually no affinity for opiate, benzodiazepine, phencyclidine (PCP), or N-methyl-D-aspartic acid (NMDA) receptors.

Venlafaxine was not found to have any significant CNS stimulant activity in rodents. In primate drug discrimination studies, venlafaxine showed no significant stimulant or depressant abuse liability.

Discontinuation effects have been reported in patients receiving venlafaxine [see Dosage and Administration (2.10) and Warnings and Precautions (5.7)].

10 OVERDOSAGE

Human Experience

During the premarketing evaluations of Effexor XR (for MDD, GAD, SAD, and PD) and Effexor (for MDD), there were twenty reports of acute overdosage with Effexor (6 and 14 reports in Effexor XR and Effexor patients, respectively), either alone or in combination with other drugs and/or alcohol.

Somnolence was the most commonly reported symptom. Among the other reported symptoms were paresthesia of all four limbs, moderate dizziness, nausea, numb hands and feet, and hot-cold spells 5 days after the overdose. In most cases, no signs or symptoms were associated with overdose. The majority of the reports involved ingestion in which the total dose of venlafaxine taken was estimated to be no more than several-fold higher than the usual therapeutic dose. One patient who ingested 2.75 g of venlafaxine was observed to have two generalized convulsions and a prolongation of QTc to 500 msec, compared with 405 msec at baseline. Mild sinus tachycardia was reported in two of the other patients.

Actions taken to treat the overdose included no treatment, hospitalization and symptomatic treatment, and hospitalization plus treatment with activated charcoal. All patients recovered.

In postmarketing experience, overdose with venlafaxine has occurred predominantly in combination with alcohol and/or other drugs. The most commonly reported events in overdosage include tachycardia, changes in level of consciousness (ranging from somnolence to coma), mydriasis, seizures, and vomiting. Electrocardiogram changes (e.g., prolongation of QT interval, bundle branch block, QRS prolongation), ventricular tachycardia, bradycardia, hypotension, rhabdomyolysis, vertigo, liver necrosis, serotonin syndrome, and death have been reported.

Published retrospective studies report that venlafaxine overdosage may be associated with an increased risk of fatal outcomes compared to that observed with SSRI antidepressant products, but lower than that for tricyclic antidepressants. Epidemiological studies have shown that venlafaxine-treated patients have a higher preexisting burden of suicide risk factors than SSRI-treated patients. The extent to which the finding of an increased risk of fatal outcomes can be attributed to the toxicity of venlafaxine in overdosage, as opposed to some characteristic(s) of venlafaxine-treated patients, is not clear. Prescriptions for Effexor XR should be written for the smallest quantity of capsules consistent with good patient management, in order to reduce the risk of overdose.

Management of Overdosage

No specific antidotes for Effexor XR are known. In managing overdosage, consider the possibility of multiple drug involvement. Consider contacting a Poison Center (1-800-222-1222) or a medical toxicologist for overdosage management recommendations for Effexor XR.

11 DESCRIPTION

Effexor XR is an extended-release capsule for once-a-day oral administration that contains venlafaxine hydrochloride, a serotonin and norepinephrine reuptake inhibitor (SNRI).

Venlafaxine is designated (R/S)-1-[2-(dimethylamino)-1-(4-methoxyphenyl)ethyl] cyclohexanol hydrochloride or (±)-1-[α- [(dimethylamino)methyl]-p-methoxybenzyl] cyclohexanol hydrochloride and has the empirical formula of C17H27NO2 HCl. Its molecular weight is 313.86. The structural formula is shown as follows:

Venlafaxine hydrochloride is a white to off-white crystalline solid, with a solubility of 572 mg/mL in water (adjusted to ionic strength of 0.2 M with sodium chloride). Its octanol:water (0.2 M sodium chloride) partition coefficient is 0.43.

Drug release is controlled by diffusion through the coating membrane on the spheroids and is not pH-dependent. Capsules contain venlafaxine hydrochloride equivalent to 37.5 mg, 75 mg, or 150 mg venlafaxine. Inactive ingredients consist of cellulose, ethylcellulose, gelatin, hypromellose, iron oxide, and titanium dioxide.

12 CLINICAL PHARMACOLOGY

12.1 Mechanism of Action

The mechanism of action of venlafaxine in the treatment of MDD, GAD, SAD, and PD is unclear, but is thought to be related to the potentiation of serotonin and norepinephrine in the central nervous system, through inhibition of their reuptake.

12.2 Pharmacodynamics

In vitro studies have demonstrated that venlafaxine and its active metabolite, O-desmethylvenlafaxine (ODV), are potent and selective inhibitors of neuronal serotonin and norepinephrine reuptake and weak inhibitors of dopamine reuptake. Venlafaxine and ODV have no significant affinity for muscarinic-cholinergic, H1-histaminergic, or α1-adrenergic receptors in vitro. Pharmacologic activity at these receptors is hypothesized to be associated with the various anticholinergic, sedative, and cardiovascular effects seen with other psychotropic drugs. Venlafaxine and ODV do not possess monoamine oxidase (MAO) inhibitory activity.

Cardiac Electrophysiology

The effect of venlafaxine on the QT interval was evaluated in a randomized, double-blind, placebo- and positive-controlled three-period crossover thorough QT study in 54 healthy adult subjects. No significant QT prolongation effect of venlafaxine at 450 mg (2 times the maximum recommended dosage) was detected.

12.3 Pharmacokinetics

Venlafaxine and ODV steady-state concentrations are reached within 3 days. Venlafaxine and ODV exhibited linear kinetics over the dosage range of 75 to 450 mg per day (0.33 to 2 times the maximum recommended dosage). Time of administration (AM versus PM) did not affect the pharmacokinetics of venlafaxine and ODV from the 75 mg Effexor XR capsule.

Absorption

Venlafaxine is well absorbed. On the basis of mass balance studies, at least 92% of a single oral dose of venlafaxine is absorbed. The absolute bioavailability of venlafaxine is approximately 45%.

Administration of Effexor XR (150 mg once daily) generally resulted in lower Cmax and later Tmax values than for Effexor administered twice daily (Table 17). When equal daily doses of venlafaxine were administered as either an immediate-release tablet or the extended-release capsule, the exposure to both venlafaxine and ODV was similar for the two treatments, and the fluctuation in plasma concentrations was slightly lower with the Effexor XR capsule. Therefore, Effexor XR provides a slower rate of absorption, but the same extent of absorption compared with the immediate-release tablet.

Table 17: Comparison of Cmax and Tmax Values for Venlafaxine and ODV Following Oral Administration of Effexor XR and Effexor (Immediate-Release)
 | Venlafaxine |  | ODV
 | Cmax (ng/mL) | Tmax (h) | Cmax (ng/mL) | Tmax (h)
Effexor XR (150 mg once daily) | 150 | 5.5 | 260 | 9
Effexor (75 mg twice daily) | 225 | 2 | 290 | 3

Effect of Food

Food did not affect the bioavailability of venlafaxine or its active metabolite, ODV.

Distribution

Venlafaxine is 27% and ODV is 30% bound to plasma proteins. The apparent volume of distribution at steady-state is 7.5 ± 3.7 L/kg for venlafaxine and 5.7 ± 1.8 L/kg for ODV.

Elimination

Mean ± SD plasma apparent clearance at steady-state is 1.3 ± 0.6 L/h/kg for venlafaxine and 0.4 ± 0.2 L/h/kg for ODV. The apparent elimination half-life is 5 ± 2 hours for venlafaxine and 11 ± 2 hours for ODV.

Metabolism

Following absorption, venlafaxine undergoes extensive presystemic metabolism in the liver, primarily to ODV, but also to N-desmethylvenlafaxine, N,O-didesmethylvenlafaxine, and other minor metabolites. In vitro studies indicate that the formation of ODV is catalyzed by CYP2D6; this has been confirmed in a clinical study showing that patients with low CYP2D6 levels (poor metabolizers) had increased levels of venlafaxine and reduced levels of ODV compared to people with normal CYP2D6 levels (extensive metabolizers) (see Figure 1).

Excretion

Approximately 87% of a venlafaxine dose is recovered in the urine within 48 hours as unchanged venlafaxine (5%), unconjugated ODV (29%), conjugated ODV (26%), or other minor inactive metabolites (27%).

Specific Populations

The effect of intrinsic patient factors on the pharmacokinetics of venlafaxine and its active metabolite ODV is presented in Figure 1.

Figure 1: Pharmacokinetics of Venlafaxine and Active Metabolite O-desmethylvenlafaxine (ODV) in Special Populations

ODV=O-desmethylvenlafaxine; AUC=area under the curve; Cmax=peak plasma concentrations.

* Similar effect is expected with strong CYP2D6 inhibitors.

Drug Interaction Studies

Clinical Studies

Effect of Other Drugs on Effexor XR and Active Metabolite ODV

The effects of other drugs on the exposure of venlafaxine and ODV are summarized in Figure 2.

Figure 2: Effect of Other Drugs on the Pharmacokinetics of Venlafaxine and Active Metabolite O‑desmethylvenlafaxine (ODV)

ODV=O-desmethylvenlafaxine; AUC=area under the curve; Cmax=peak plasma concentrations; EM’s=extensive metabolizers; PM’s=poor metabolizers.

Effect of Effexor XR on Other Drugs

The effects of Effexor XR on the exposure of other drugs are summarized in Figure 3.

Figure 3: Effect of Venlafaxine on the Pharmacokinetics of Interacting Drugs and their Active Metabolites

AUC=area under the curve; Cmax=peak plasma concentrations; OH=hydroxyl.

* Data for 2-OH desipramine were not plotted to enhance clarity; the fold change and 90% CI for Cmax and AUC of 2-OH desipramine were 6.6 (5.5, 7.9) and 4.4 (3.8, 5.0), respectively.

Note: *Administration of venlafaxine in a stable regimen did not exaggerate the psychomotor and psychometric effects induced by ethanol in these same subjects when they were not receiving venlafaxine.

13 NONCLINICAL TOXICOLOGY

13.1 Carcinogenesis, Mutagenesis, Impairment of Fertility

Carcinogenesis

Tumors were not increased by venlafaxine treatment in mice or rats. Venlafaxine was given by oral gavage to mice for 18 months at doses up to 120 mg/kg per day, which was 1.7 times the maximum recommended human dose on a mg/m^2 basis. Venlafaxine was also given to rats by oral gavage for 24 months at doses up to 120 mg/kg per day. In rats receiving the 120 mg/kg dose, plasma concentrations of venlafaxine at necropsy were 1 times (male rats) and 6 times (female rats) the plasma concentrations of patients receiving the maximum recommended human dose. Plasma levels of the ODV were lower in rats than in patients receiving the maximum recommended dose. ODV, the major human metabolite of venlafaxine, administered by oral gavage to mice and rats for 2 years did not increase the incidence of tumors in either study. Mice received ODV at dosages up to 500/300 mg/kg/day (dosage lowered after 45 weeks of dosing). The exposure at the 300 mg/kg/day dose is 9 times that of a human dose of 225 mg/day. Rats received ODV at dosages up to 300 mg/kg/day (males) or 500 mg/kg/day (females). The exposure at the highest dose is approximately 8 (males) or 11 (females) times that of a human dose of 225 mg/day.

Mutagenesis

Venlafaxine and the major human metabolite, ODV, were not mutagenic in the Ames reverse mutation assay in Salmonella bacteria or the Chinese hamster ovary/HGPRT mammalian cell forward gene mutation assay. Venlafaxine was also not mutagenic or clastogenic in the in vitro BALB/c-3T3 mouse cell transformation assay, the sister chromatid exchange assay in cultured Chinese hamster ovary cells, or in the in vivo chromosomal aberration assay in rat bone marrow. ODV was not clastogenic in the in vitro Chinese hamster ovary cell chromosomal aberration assay or in the in vivo chromosomal aberration assay in rats.

Impairment of Fertility

Reproduction and fertility studies of venlafaxine in rats showed no adverse effects of venlafaxine on male or female fertility at oral doses of up to 2 times the maximum recommended human dose of 225 mg/day on a mg/m^2 basis. However, when desvenlafaxine succinate, the major human metabolite of venlafaxine, was administered orally to male and female rats, fertility was reduced at the high dose of 300 mg/kg/day, which is 10 (males) and 19 (females) times the AUC exposure at an adult human dose of 100 mg per day. There was no effect on fertility at 100 mg/kg/day, which is 3 (males) or 5 (females) times the AUC exposure at an adult human dose of 100 mg per day. These studies did not address reversibility of the effect on fertility. The relevance of these findings to humans is not known.

14 CLINICAL STUDIES

14.1 Major Depressive Disorder

The efficacy of Effexor XR (venlafaxine hydrochloride) extended-release capsules as a treatment for Major Depressive Disorder (MDD) was established in two placebo-controlled, short-term (8 weeks for study 1; 12 weeks for study 2), flexible-dose studies, with doses starting at 75 mg per day and ranging to 225 mg per day in adult outpatients meeting DSM-III-R or DSM-IV criteria for MDD. In moderately depressed outpatients, the initial dose of venlafaxine was 75 mg per day. In both studies, Effexor XR demonstrated superiority over placebo on the primary efficacy measure defined as change from baseline in the HAM-D-21 total score to the endpoint visit, Effexor XR also demonstrated superiority over placebo on the key secondary efficacy endpoint, the Clinical Global Impressions (CGI) Severity of Illness scale. Examination of gender subsets of the population studied did not reveal any differential responsiveness on the basis of gender.

A 4-week study of inpatients meeting DSM-III-R criteria for MDD with melancholia utilizing Effexor in a range of 150 to 375 mg per day (divided in a three-times-a-day schedule) demonstrated superiority of Effexor over placebo based on the HAM-D-21 total score. The mean dose in completers was 350 mg per day (study 3).

In a longer-term study, adult outpatients with MDD who had responded during an 8-week open-label study on Effexor XR (75, 150, or 225 mg, once daily every morning) were randomized to continuation of their same Effexor XR dose or to placebo, for up to 26 weeks of observation for relapse. Response during the open-label phase was defined as a CGI Severity of Illness item score of ≤3 and a HAM-D-21 total score of ≤10 at the day 56 evaluation. Relapse during the double-blind phase was defined as follows: (1) a reappearance of major depressive disorder as defined by DSM-IV criteria and a CGI Severity of Illness item score of ≥4 (moderately ill), (2) 2 consecutive CGI Severity of Illness item scores of ≥4, or (3) a final CGI Severity of Illness item score of ≥4 for any patient who withdrew from the study for any reason. Patients receiving continued Effexor XR treatment experienced statistically significantly lower relapse rates over the subsequent 26 weeks compared with those receiving placebo (study 4).

In a second longer term trial, adult outpatients with MDD, recurrent type, who had responded (HAM-D-21 total score ≤12 at the day 56 evaluation) and continued to be improved [defined as the following criteria being met for days 56 through 180: (1) no HAM-D-21 total score ≥20; (2) no more than 2 HAM-D-21 total scores >10, and (3) no single CGI Severity of Illness item score ≥4 (moderately ill)] during an initial 26 weeks of treatment on Effexor [100 to 200 mg per day, on a twice daily schedule] were randomized to continuation of their same Effexor dose or to placebo. The follow-up period to observe patients for relapse, defined as a CGI Severity of Illness item score ≥4, was for up to 52 weeks. Patients receiving continued Effexor treatment experienced statistically significantly lower relapse rates over the subsequent 52 weeks compared with those receiving placebo (study 5).

Table 18: Primary Efficacy Results for Studies in Major Depressive Disorder in Adults (Studies 1, 2, 3)
Study Number | Treatment Group |  | Primary Efficacy Measure: HAM-D Score
 |  | Mean Baseline Score (SD) | LS Mean Change from Baseline | Placebo Subtracted Difference [Difference (drug minus placebo) in least-squares mean change from baseline.] (95%CI)
Study 1 | Effexor (XR 75-225 mg/day) [Doses statistically significantly superior to placebo.] | 24.5 | -11.7 | -4.45 (-6.66, -2.25)
Study 1 | Placebo | 23.6 | -7.24 | -
Study 2 | Effexor (XR 75-225 mg/day) | 24.5 | -15.11 | -6.40 (-8.45, -4.34)
Study 2 | Placebo | 24.9 | -8.71
Study 3 | Effexor (IR 150-375 mg/day) | 28.2 (0.5) | -14.9 | -10.2 (-14.4, -6.0)
Study 3 | Placebo | 28.6 (0.6) | -4.7 | -
SD=standard deviation; LS Mean=least-squares mean; CI=confidence interval.

14.2 Generalized Anxiety Disorder

The efficacy of Effexor XR as a treatment for Generalized Anxiety Disorder (GAD) was established in two 8-week, placebo-controlled, fixed-dose studies (75 to 225 mg per day), one 6-month, placebo-controlled, flexible-dose study (75 to 225 mg per day), and one 6-month, placebo-controlled, fixed-dose study (37.5, 75, and 150 mg per day) in adult outpatients meeting DSM-IV criteria for GAD.

In one 8-week study, Effexor XR demonstrated superiority over placebo for the 75, 150, and 225 mg per day doses as measured by the Hamilton Rating Scale for Anxiety (HAM-A) total score, both the HAM-A anxiety and tension items, and the Clinical Global Impressions (CGI) scale. However, the 75 and 150 mg per day doses were not as consistently effective as the highest dose (study 1). A second 8-week study evaluating doses of 75 and 150 mg per day and placebo showed that both doses were more effective than placebo on some of these same outcomes; however, the 75 mg per day dose was more consistently effective than the 150 mg per day dose (study 2). A dose-response relationship for effectiveness in GAD was not clearly established in the 75 to 225 mg per day dose range studied.

Two 6-month studies, one evaluating Effexor XR doses of 37.5, 75, and 150 mg per day (study 3) and the other evaluating Effexor XR doses of 75 to 225 mg per day (study 4), showed that daily doses of 75 mg or higher were more effective than placebo on the HAM-A total, both the HAM-A anxiety and tension items, and the CGI scale during 6 months of treatment. While there was also evidence for superiority over placebo for the 37.5 mg per day dose, this dose was not as consistently effective as the higher doses.

Examination of gender subsets of the population studied did not reveal any differential responsiveness on the basis of gender.

Table 19: Primary Efficacy Results for Studies in Generalized Anxiety Disorder in Adults (Studies 1, 2, 3, 4)
Study Number | Treatment Group | Primary Efficacy Measure: HAM-A Score
 |  | Mean Baseline Score (SD) | LS Mean Change from Baseline (SE) [Doses statistically significantly superior to placebo.] | Placebo Subtracted Difference [Difference (drug minus placebo) in least-squares mean change from baseline.] (95% CI)
Study 1 | Ven XR 75 mg | 24.7 | -11.1 (0.95) | -1.5 (-3.8, 0.8)
Study 1 | Ven XR 150 mg | 24.5 | -11.7 (0.87) | -2.2 (-4.5, 0.1)
Study 1 | Ven XR 225 mg | 23.6 | -12.1 (0.81) | -2.6 (-4.9, -0.3)
Study 1 | Placebo | 24.1 | -9.5 (0.85)
Study 2 | Ven XR 75 mg | 23.7 | -10.6 (0.82) | -2.6 (-4.6, -0.5)
Study 2 | Ven XR 150 mg | 23.0 | -9.8 (0.86) | -1.7 (-3.8, 0.3)
Study 2 | Placebo | 23.7 | -8.0 (0.73)
Study 3 | Ven XR 37.5 mg | 26.6 (0.4) | -13.8 | -2.8 (-5.1, -0.6)
Study 3 | Ven XR 75 mg | 26.3 (0.4) | -15.5 | -4.6 (-6.9, -2.3)
Study 3 | Ven XR150 mg | 26.3 (0.4) | -16.4 | -5.5 (-7.8, -3.1)
Study 3 | Placebo | 26.7 (0.5) | -11.0
Study 4 | Ven XR 75-225 mg | 25.0 | -13.4 (0.79) | -4.7 (-6.6, -2.9)
Study 4 | Placebo | 24.9 | -8.7 (0.70)
SD=standard deviation; SE=standard error; LS Mean=least-squares mean; CI=confidence interval.

14.3 Social Anxiety Disorder (Also Known as Social Phobia)

The efficacy of Effexor XR as a treatment for Social Anxiety Disorder (SAD) was established in four double-blind, parallel-group, 12-week, multicenter, placebo-controlled, flexible-dose studies (studies 1-4) and one double-blind, parallel-group, 6-month, placebo-controlled, fixed/flexible-dose study, which included doses in a range of 75 to 225 mg per day in adult outpatients meeting DSM-IV criteria for SAD (study 5).

In these five studies, Effexor XR was statistically significantly more effective than placebo on change from baseline to endpoint on the Liebowitz Social Anxiety Scale (LSAS) total score. There was no evidence for any greater effectiveness of the 150 to 225 mg per day group compared to the 75 mg per day group in the 6-month study.

Examination of subsets of the population studied did not reveal any differential responsiveness on the basis of gender. There was insufficient information to determine the effect of age or race on outcome in these studies.

Table 20: Primary Efficacy Results for Studies in Social Anxiety Disorder in Adults (Studies 1, 2, 3, 4, 5)
Study Number | Treatment Group | Primary Efficacy Measure: LSAS Score
 |  | Mean Baseline Score (SD) | LS Mean Change from Baseline (SE) | Placebo Subtracted Difference [Difference (drug minus placebo) in least-squares mean change from baseline.] (95% CI)
Study 1 | Ven XR (75-225 mg) [Doses statistically significantly superior to placebo.] | 91.1 | -31.0 (2.22) | 11.2 (-5.3, -17.1)
Study 1 | Placebo | 86.7 | -19.9 (2.22) | -
Study 2 | Ven XR (75-225 mg) | 90.8 | -32.8 (2.69) | -10.7 (-3.7, -17.6)
Study 2 | Placebo | 87.4 | -22.1 (2.66) | -
Study 3 | Ven XR (75-225 mg) | 83.2 | -36.0 (2.35) | -16.9 (-22.6, -11.2)
Study 3 | Placebo | 83.6 | -19.1 (2.40) | -12.7 (-6.5, -19.0)
Study 4 | Ven XR (75-225 mg) | 86.2 | -35.0 (2.64) | -14.6 (-21.8, -7.4)
Study 4 | Placebo | 86.1 | -22.2 (2.47)
Study 5 | Ven XR 75 mg | 91.8 | -38.1 (3.16) | -14.6 (-21.8, -7.4)
Study 5 | Ven XR (150-225 mg) | 86.2 | -37.6 (3.05) | -14.1 (-21.3, -6.9)
Study 5 | Placebo | 89.3 | -23.5 (3.08)
SD=standard deviation; SE=standard error; LS Mean=least-squares mean; CI=confidence interval.

14.4 Panic Disorder

The efficacy of Effexor XR as a treatment for Panic Disorder (PD) was established in two double-blind, 12-week, multicenter, placebo-controlled studies in adult outpatients meeting DSM-IV criteria for PD, with or without agoraphobia. Patients received fixed doses of 75 or 150 mg per day in one study (study 1) and 75 or 225 mg per day in the other study (study 2).

Efficacy was assessed on the basis of outcomes in three variables: (1) percentage of patients free of full-symptom panic attacks on the Panic and Anticipatory Anxiety Scale (PAAS); (2) mean change from baseline to endpoint on the Panic Disorder Severity Scale (PDSS) total score; and (3) percentage of patients rated as responders (much improved or very much improved) on the Clinical Global Impressions (CGI) Improvement scale. In these two studies, Effexor XR was statistically significantly more effective than placebo (for each fixed dose) on all three endpoints, but a dose-response relationship was not clearly established.

Examination of subsets of the population studied did not reveal any differential responsiveness on the basis of gender. There was insufficient information to determine the effect of age or race on outcome in these studies.

In a longer term study (study 3), adult outpatients meeting DSM-IV criteria for PD who had responded during a 12-week open phase with Effexor XR (75 to 225 mg per day) were randomly assigned to continue the same Effexor XR dose (75, 150, or 225 mg) or switch to placebo for observation for relapse under double-blind conditions. Response during the open phase was defined as ≤ 1 full-symptom panic attack per week during the last 2 weeks of the open phase and a CGI Improvement score of 1 (very much improved) or 2 (much improved). Relapse during the double-blind phase was defined as having 2 or more full-symptom panic attacks per week for 2 consecutive weeks or having discontinued due to loss of effectiveness as determined by the investigators during the study. Randomized patients were in response status for a mean time of 34 days prior to being randomized. In the randomized phase following the 12-week open-label period, patients receiving continued Effexor XR experienced a statistically significantly longer time to relapse.

Table 21: Primary Efficacy Results for Studies in Panic Disorder in Adults (Studies 1 and 2)
Study Treatment Group; Number |  | Primary Efficacy Measure: Whether Free of Full-symptom Panic Attacks
 |  | Percent of Patients Free of Full Symptom Panic Attack | Adjusted Odds Ratio [Odds ratio (drug to placebo) in terms of probability of free of full-symptom panic attacks based on logistic regression model. 95% CI: 95% confidence interval without adjusting for multiple dose arms.] to Placebo | Adjusted Odds Ratio 95% Confidence Interval
Study 1 | Ven XR 75 mg [Doses statistically significantly superior to placebo.]; Ven XR 150 mg; Placebo | 54.1% (85/157); 61.4% (97/158); 34.4% (53/154) | 2.268; 3.035; -- | (1.43, 3.59); (1.91, 4.82); --
Study 2 | Ven XR 75 mg; Ven XR 225 mg; Placebo | 64.1% (100/156); 70.0% (112/160); 46.5% (73/157) | 2.350; 2.890; -- | (1.46, 3.78); (1.80, 4.64); --

16 HOW SUPPLIED/STORAGE AND HANDLING

Effexor XR® is available as:

- 37.5 mg, grey cap/peach body with “W” and “Effexor XR” on the cap and “37.5” on the body.
  NDC 58151-125-93, bottle of 30 capsules in unit-of-use package.
  NDC 58151-125-77, bottle of 90 capsules in unit-of-use package.
- 75 mg, peach cap and body with “W” and “Effexor XR” on the cap and “75” on the body.
  NDC 58151-126-93, bottle of 30 capsules in unit-of-use package.
  NDC 58151-126-77, bottle of 90 capsules in unit-of-use package.
- 150 mg, dark orange cap and body with “W” and “Effexor XR” on the cap and “150” on the body.
  NDC 58151-127-93, bottle of 30 capsules in unit-of-use package.
  NDC 58151-127-77, bottle of 90 capsules in unit-of-use package.

Store at controlled room temperature, 20° to 25°C (68° to 77°F).

17 PATIENT COUNSELING INFORMATION

Advise the patient to read the FDA-approved patient labeling (Medication Guide).

Suicidal Thoughts and Behaviors

Advise patients and caregivers to look for the emergence of suicidality, especially early during treatment and when the dose is adjusted up or down, and instruct them to report such symptoms to the healthcare provider [see Boxed Warning and Warnings and Precautions (5.1)].

Concomitant Medication

Instruct patients not to take Effexor XR with an MAOI or within 14 days of stopping an MAOI [see Contraindications (4)].

Serotonin Syndrome

Caution patients about the risk of serotonin syndrome, particularly with the concomitant use of Effexor XR with other serotonergic drugs including triptans, tricyclic antidepressants, opioids, lithium, tryptophan, buspirone, amphetamines, St. John’s Wort, and with drugs that impair metabolism of serotonin (in particular, MAOIs, both those intended to treat psychiatric disorders and also others, such as linezolid). Instruct patients to contact their healthcare provider or report to the emergency room if they experience signs or symptoms of serotonin syndrome [see Warnings and Precautions (5.2) and Drug Interactions (7.1)].

Elevated Blood Pressure

Advise patients that they should have regular monitoring of blood pressure when taking Effexor XR [see Warnings and Precautions (5.3)].

Increased Risk of Bleeding

Inform patients about the concomitant use of Effexor XR with NSAIDs, aspirin, other antiplatelet drugs, warfarin, or other drugs that affect coagulation because the combined use has been associated with an increased risk of bleeding. Advise patients to inform their health care providers if they are taking or planning to take any prescription or over-the-counter medications that increase the risk of bleeding [see Warnings and Precautions (5.4)].

Activation of Mania/Hypomania

Advise patients, their families and caregivers to observe for signs of activation of mania/hypomania and instruct them to report such symptoms to the healthcare provider [see Warnings and Precautions (5.6)].

Cardiovascular/Cerebrovascular Disease

Caution is advised in administering Effexor XR to patients with cardiovascular, cerebrovascular, or lipid metabolism disorders [see Adverse Reactions (6.1)].

Serum Cholesterol and Triglyceride Elevation

Advise patients that elevations in total cholesterol, LDL and triglycerides may occur and that measurement of serum lipids may be considered [see Adverse Reactions (6.1)].

Discontinuation Syndrome

Advise patients not to abruptly stop taking Effexor XR without talking first with their healthcare provider. Patients should be aware that discontinuation effects may occur when stopping Effexor XR and they should monitor for discontinuation symptoms [see Warnings and Precautions (5.7) and Adverse Reactions (6.1)].

Sexual Dysfunction

Advise patients that use of Effexor XR may cause symptoms of sexual dysfunction in both male and female patients. Inform patients that they should discuss any changes in sexual function and potential management strategies with their healthcare provider [see Warnings and Precautions (5.13)].

Interference with Cognitive and Motor Performance

Caution patients about operating hazardous machinery, including automobiles, until they are reasonably certain that Effexor XR therapy does not adversely affect their ability to engage in such activities.

Alcohol

Advise patients to avoid alcohol while taking Effexor XR [see Drug Interactions (7.2)].

Allergic Reactions

Advise patients to notify their healthcare provider if they develop allergic phenomena such as rash, hives, swelling, or difficulty breathing [see Contraindications (4) and Adverse Reactions (6.2)].

Pregnancy

Advise patients to notify their healthcare provider if they become pregnant or intend to become pregnant during treatment with Effexor XR. Advise patients that Effexor XR use during mid to late pregnancy may lead to an increased risk for preeclampsia and may increase the risk for neonatal complications requiring prolonged hospitalization, respiratory support, and tube feeding. Advise patients that there is a pregnancy exposure registry that monitors pregnancy outcomes in women exposed to Effexor XR during pregnancy [see Use in Specific Populations (8.1)].

Residual Spheroids

Effexor XR contains spheroids, which release the drug slowly into the digestive tract. The insoluble portion of these spheroids is eliminated, and patients may notice spheroids passing in the stool or via colostomy. Patients should be informed that the active medication has already been absorbed by the time the patient sees the spheroids.

Distributed by:
Viatris Specialty LLC
Morgantown, WV 26505 U.S.A.

Made in Ireland

© 2023 Viatris Inc.

EFFEXOR XR is a registered trademark of Viatris Specialty LLC, a Viatris Company.

UPJ:EFFXRXR:R1m

MEDICATION GUIDE

EFFEXOR XR (e-fex-or XR)
(venlafaxine extended-release)
capsules

What is the most important information I should know about EFFEXOR XR?

EFFEXOR XR may cause serious side effects, including:

- Increased risk of suicidal thoughts and actions. EFFEXOR XR and other antidepressant medicines may increase suicidal thoughts and actions in some children, adolescents, and young adults, especially within the first few months of treatment or when the dose is changed. EFFEXOR XR is not for use in children.
  - Depression or other serious mental illnesses are the most important causes of suicidal thoughts or actions.
How can I watch for and try to prevent suicidal thoughts and actions in myself or a family member?
  1. Pay close attention to any changes, especially sudden changes, in mood, behaviors, thoughts, or feelings. This is very important when an antidepressant medicine is started or when the dose is changed.
  2. Call your healthcare provider right away to report new or sudden changes in mood, behavior, thoughts, or feelings.
  3. Keep all follow-up visits with your healthcare provider as scheduled. Call your healthcare provider between visits as needed, especially if you have concerns about symptoms.
Call your healthcare provider or get emergency help right away if you or a family member have any of the following symptoms, especially if they are new, worse, or worry you:

- attempts to commit suicide
- acting aggressive, being angry, or violent
- new or worse depression
- panic attacks
- new or worse irritability
- an extreme increase in activity or talking (mania)

- thoughts about suicide or dying
- acting on dangerous impulses
- new or worse anxiety
- feeling very agitated or restless
- trouble sleeping
- other unusual changes in behavior or mood

What is EFFEXOR XR?

EFFEXOR XR is a prescription medicine used to treat adults with:

- a certain type of depression called Major Depressive Disorder (MDD)
- Generalized Anxiety Disorder (GAD)
- Social Anxiety Disorder (SAD)
- Panic Disorder (PD)

It is not known if EFFEXOR XR is safe and effective for use in children.

Do not take EFFEXOR XR if you:

- are allergic to venlafaxine hydrochloride, desvenlafaxine succinate, or any of the ingredients in EFFEXOR XR. See the end of this Medication Guide for a complete list of ingredients in EFFEXOR XR.
- take a Monoamine Oxidase Inhibitor (MAOI)
- have stopped taking an MAOI in the last 14 days
- are being treated with the antibiotic linezolid or intravenous methylene blue

Ask your healthcare provider or pharmacist if you are not sure if you take an MAOI, including MAOIs such as linezolid or intravenous methylene blue.

Do not start taking an MAOI for at least 7 days after you stop treatment with EFFEXOR XR.

Before taking EFFEXOR XR tell your healthcare provider about all your medical conditions, including if you:

- have, or have a family history of suicide, bipolar disorder, depression, mania or hypomania
- have high blood pressure
- have heart problems
- have cerebrovascular problems or had a stroke
- have or have had bleeding problems
- have high pressure in the eye (glaucoma)
- have high cholesterol or high triglycerides
- have kidney or liver problems
- have or had seizures or convulsions
- have low sodium levels in your blood
- have lung problems
- drink alcohol
- are pregnant or plan to become pregnant. EFFEXOR XR may harm your unborn baby. Talk to your healthcare provider about the risk to you and your unborn baby if you take EFFEXOR XR during pregnancy.
  - Tell your healthcare provider if you become pregnant or think you are pregnant during treatment with EFFEXOR XR.
  - Pregnancy Exposure Registry. There is a pregnancy registry for women who are exposed to EFFEXOR XR during pregnancy. The purpose of the registry is to collect information about the health of you and your baby. If you become pregnant during treatment with EFFEXOR XR, talk to your healthcare provider about registering with the National Pregnancy Registry for Antidepressants. You can register by calling 1-844-405-6185 or by visiting online at https://womensmentalhealth.org/research/pregnancyregistry/antidepressants.
- are breastfeeding or plan to breastfeed. EFFEXOR XR passes into your breast milk and may harm your baby. Talk to your healthcare provider about the best way to feed your baby during treatment with EFFEXOR XR.

Tell your healthcare provider about all the medicines you take, including prescription and over-the-counter medicines, vitamins, and herbal supplements.

EFFEXOR XR and other medicines may affect each other causing possible serious side effects. EFFEXOR XR may affect the way other medicines work and other medicines may affect the way EFFEXOR XR works.

Especially tell your healthcare provider if you take:

- medicines to treat migraine headaches known as triptans
- tricyclic antidepressants
- lithium
- tramadol, fentanyl, meperidine, methadone, or other opioids
- tryptophan
- buspirone
- amphetamines
- St. John’s Wort
- phentermine
- other medicines containing desvenlafaxine or venlafaxine
- medicines that can affect blood clotting such as aspirin, nonsteroidal anti-inflammatory drugs (NSAIDs), warfarin

Ask your healthcare provider if you are not sure if you are taking any of these medicines. Your healthcare provider can tell you if it is safe to take EFFEXOR XR with your other medicines.

Do not start or stop any other medicines during treatment with EFFEXOR XR without first talking to your healthcare provider. Stopping EFFEXOR XR suddenly may cause you to have serious side effects. See “What are the possible side effects of EFFEXOR XR?”

Know the medicines you take. Keep a list of them to show to your healthcare provider and pharmacist when you get a new medicine.

How should I take EFFEXOR XR?

- Take EFFEXOR XR exactly as your healthcare provider tells you to. Do not change your dose or stop taking EFFEXOR XR without first talking to your healthcare provider.
- Your healthcare provider may need to change the dose of EFFEXOR XR until it is the right dose for you.
- Take EFFEXOR XR 1 time each day with food.
- EFFEXOR may be taken either in the morning or in the evening, but take it the same way each time.
- Swallow EFFEXOR XR whole with fluid. Do not divide, crush, chew, or dissolve EFFEXOR XR.
- If you cannot swallow EFFEXOR XR capsules whole, the EFFEXOR XR capsules may be opened and the entire contents sprinkled on a spoonful of applesauce.
  - Swallow the EFFEXOR XR and applesauce mixture right away without chewing.
  - Follow with a glass of water to make sure you have swallowed all of the EFFEXOR XR pellets.
- If you take too much EFFEXOR XR, call your healthcare provider or poison control center at 1-800-222-1222 or go to the nearest hospital emergency room right away.

What should I avoid while taking EFFEXOR XR?

- Do not drive, or operate heavy machinery, or do other dangerous activities until you know how EFFEXOR XR affects you. EFFEXOR XR can make you drowsy.
- You should not drink alcohol during treatment with EFFEXOR XR. Drinking alcohol during treatment with EFFEXOR XR can increase your risk of having serious side effects.

What are the possible side effects of EFFEXOR XR?

EFFEXOR XR may cause serious side effects, including:

- See “What is the most important information I should know about EFFEXOR XR?”
- Serotonin syndrome. Taking EFFEXOR XR can cause a potentially life-threatening problem called serotonin syndrome. The risk of developing serotonin syndrome is increased when EFFEXOR XR is taken with certain other medicines. See “Do not take EFFEXOR XR if you:” Stop taking EFFEXOR XR and call your healthcare provider or go to the nearest hospital emergency room right away if you have any of the following signs and symptoms of serotonin syndrome:

- agitation
- confusion
- fast heartbeat
- dizziness
- flushing
- tremors, stiff muscles, or muscle twitching
- seizures

- seeing or hearing things that are not real (hallucinations)
- coma
- changes in blood pressure
- sweating
- high body temperature (hyperthermia)
- loss of coordination
- nausea, vomiting, diarrhea

- Increases in blood pressure. Your healthcare provider should check your blood pressure before starting treatment and regularly during treatment with EFFEXOR XR. If you have high blood pressure, it should be controlled before you start treatment with EFFEXOR XR.
- Increased risk of bleeding. Taking EFFEXOR XR with aspirin, nonsteroidal anti-inflammatory drugs (NSAIDs), or blood thinners may add to this risk. Tell your healthcare provider right away about any unusual bleeding or bruising.
- Eye problems (angle-closure glaucoma). EFFEXOR XR may cause a certain type of eye problem called angle‑closure glaucoma. You may want to undergo an eye examination to see if you are at risk and receive preventative treatment if you are. Call your healthcare provider if you have eye pain, changes in your vision, or swelling or redness in or around the eye.
- Manic episodes. Manic episodes may happen in people with bipolar disorder who take EFFEXOR XR. Symptoms may include:

- greatly increased energy
- racing thoughts
- unusually grand ideas
- talking more or faster than usual

- severe trouble sleeping
- reckless behavior
- excessive happiness or irritability

- Discontinuation syndrome. Suddenly stopping EFFEXOR XR may cause you to have serious side effects. Your healthcare provider may want to decrease your dose slowly. Symptoms may include:

- dizziness
- irritability and agitation
- anxiety
- sweating
- seizures
- ringing in your ears (tinnitus)

- nausea
- problems sleeping
- tiredness
- confusion
- electric shock sensation (paresthesia)

- headache
- diarrhea
- abnormal dreams
- changes in your mood
- hypomania

- Seizures (convulsions).
- Low sodium levels in your blood (hyponatremia). Low sodium levels can happen during treatment with EFFEXOR XR. Low sodium levels in your blood may be serious and may cause death. Elderly people may be at greater risk for this. Signs and symptoms of low sodium levels in your blood may include:
  - headache
  - difficuty concentrating
  - memory changes
  - confusion
  - weakness and unsteadiness on your feet which can lead to falls
    In severe or more sudden cases, signs and symptoms include:
  - hallucinations (seeing or hearing things that are not real)
  - fainting
  - seizures
  - coma
  - respiratory arrest
- Lung problems. Some people who have taken the medicine venlafaxine, which is the same kind of medicine as the medicine in EFFEXOR XR, have had lung problems. Symptoms of lung problems include difficulty breathing, cough, or chest discomfort. Tell your healthcare provider right away if you have any of these symptoms.
- Sexual problems (dysfunction). Taking selective serotonin reuptake inhibitors (SNRIs), including EFFEXOR XR, may cause sexual problems.
  Symptoms in males may include:
  - delayed ejaculation or inability to have an ejaculation
  - decreased sex drive
  - problems getting or keeping an erection
Symptoms in females may include:
  - decreased sex drive
  - delayed orgasm or inability to have an orgasm

Talk to your healthcare provider if you develop any changes in your sexual function or if you have any questions or concerns about sexual problems during treatment with EFFEXOR XR. There may be treatments your healthcare provider can suggest.

Your healthcare provider may tell you to stop taking EFFEXOR XR if you develop serious side effects during treatment with EFFEXOR XR.

The most common side effects of EFFEXOR XR include:

- nausea
- dry mouth
- male and female sexual problems
- loss of appetite (anorexia)

- sleepiness
- sweating
- constipation

These are not all the possible side effects of EFFEXOR XR.

Call your doctor for medical advice about side effects. You may report side effects to FDA at 1-800-FDA-1088.

How should I store EFFEXOR XR?

- Store EFFEXOR XR at room temperature between 68°F to 77°F (20°C to 25°C).
- Keep EFFEXOR XR in a dry place.

Keep EFFEXOR XR and all medicines out of the reach of children.

General information about the safe and effective use of EFFEXOR XR.

Medicines are sometimes prescribed for purposes other than those listed in a Medication Guide. Do not use EFFEXOR XR for a condition for which it was not prescribed. Do not give EFFEXOR XR to other people, even if they have the same symptoms that you have. It may harm them. You can ask your healthcare provider or pharmacist for information about EFFEXOR XR that is written for healthcare professionals.

What are the ingredients in EFFEXOR XR?

Active ingredient: venlafaxine

Inactive ingredients: cellulose, ethylcellulose, gelatin, hypromellose, iron oxide, and titanium dioxide.

Distributed by:
Viatris Specialty LLC
Morgantown, WV 26505 U.S.A.

Made in Ireland

© 2023 Viatris Inc.

EFFEXOR XR is a registered trademark of Viatris Specialty LLC, a Viatris Company.

UPJ:MG:EFFXRXR:R1m

For more information about EFFEXOR XR, call Viatris at 1-877-446-3679 (1-877-4-INFO-RX).

This Medication was approved by the U.S. Food and Drug Administration. Revised: 8/2023

PRINCIPAL DISPLAY PANEL – 37.5 mg

ALWAYS DISPENSE WITH MEDICATION GUIDE

NDC 58151-125-93

Effexor XR®
(venlafaxine HCl)
Extended-Release Capsules
37.5 mg*

30 Capsules Rx only

Store at controlled room
temperature 20° to 25°C
(68° to 77°F).

USUAL DOSAGE
See accompanying
prescribing information.

Package intended to be
dispensed as a unit.

*Each capsule contains
venlafaxine HCI equivalent
to 37.5 mg venlafaxine.

Distributed by:
Viatris Specialty LLC
Morgantown, WV 26505 U.S.A.

Made in Ireland

© 2023 Viatris Inc.

RUPJ125H

PRINCIPAL DISPLAY PANEL – 75 mg

ALWAYS DISPENSE WITH MEDICATION GUIDE

NDC 58151-126-93

Effexor XR®
(venlafaxine HCl)
Extended-Release Capsules
75 mg*

30 Capsules Rx only

Store at controlled room temperature
20° to 25°C (68° to 77°F).

USUAL DOSAGE
See accompanying prescribing information.

Package intended to be dispensed as a unit.

*Each capsule contains venlafaxine HCI
equivalent to 75 mg venlafaxine.

Distributed by:
Viatris Specialty LLC
Morgantown, WV 26505 U.S.A.

Made in Ireland

© 2023 Viatris Inc.

RUPJ126H

PRINCIPAL DISPLAY PANEL – 150 mg

ALWAYS DISPENSE WITH MEDICATION GUIDE

NDC 58151-127-93

Effexor XR®
(venlafaxine HCl)
Extended-Release Capsules
150 mg*

30 Capsules Rx only

Store at controlled room temperature
20° to 25°C (68° to 77°F).

USUAL DOSAGE
See accompanying prescribing information.

Package intended to be dispensed as a unit.

*Each capsule contains venlafaxine HCI
equivalent to 150 mg venlafaxine.

Distributed by:
Viatris Specialty LLC
Morgantown, WV 26505 U.S.A.

Made in Ireland

© 2023 Viatris Inc.

RUPJ127H